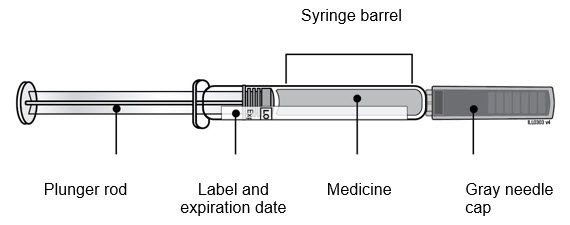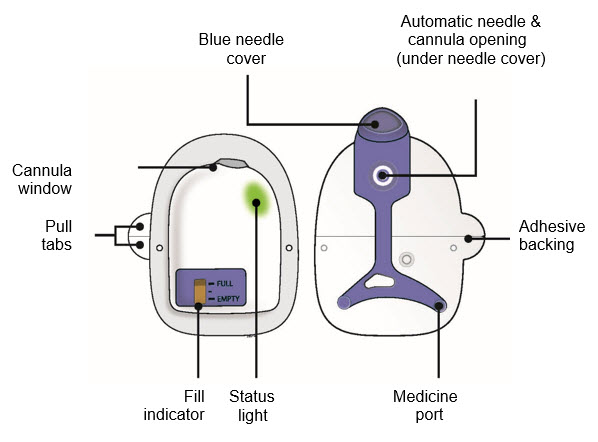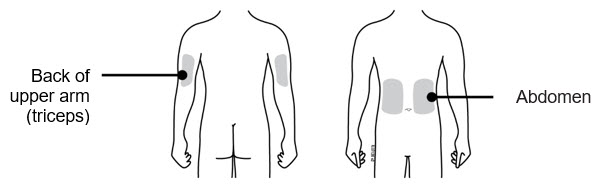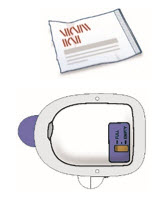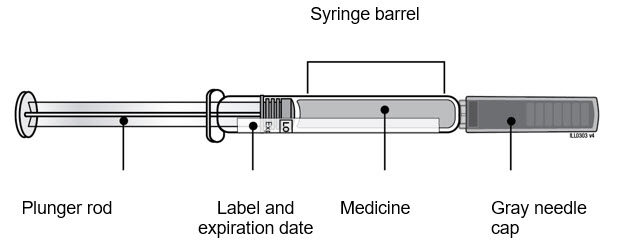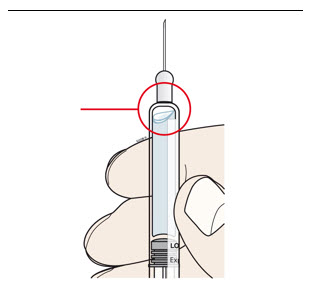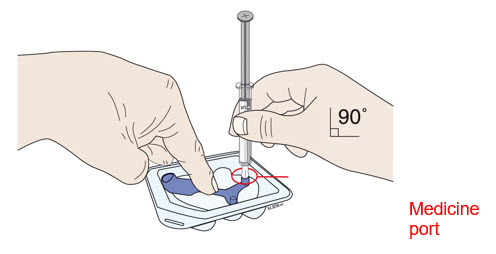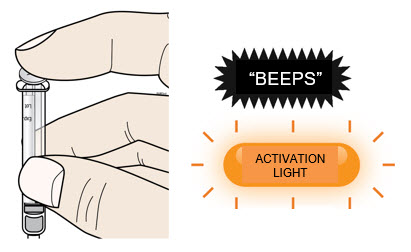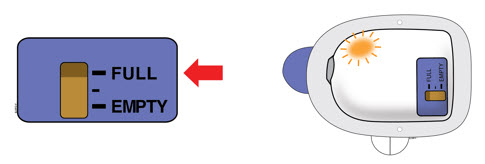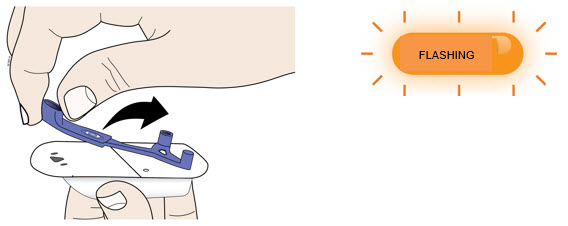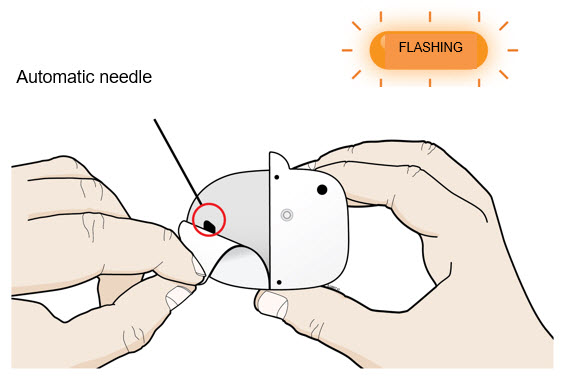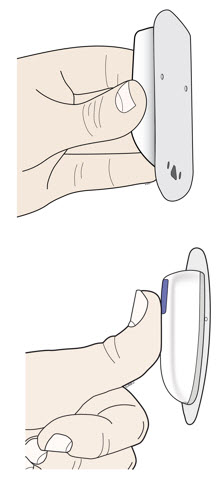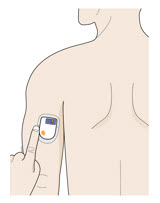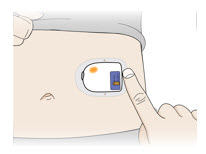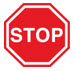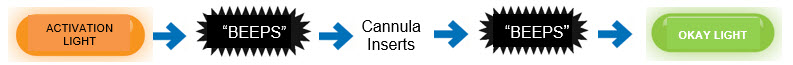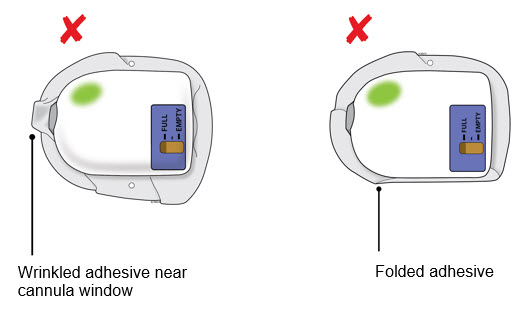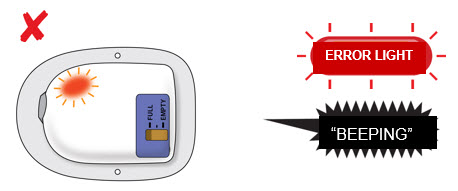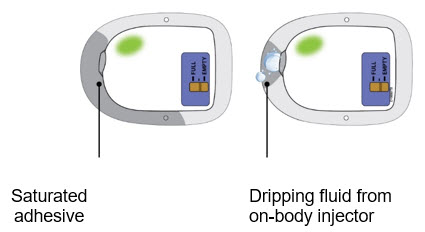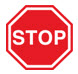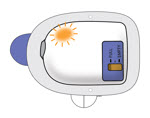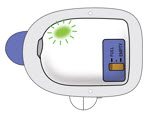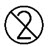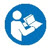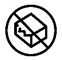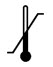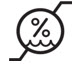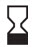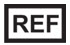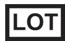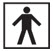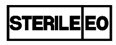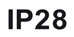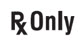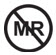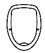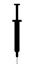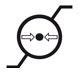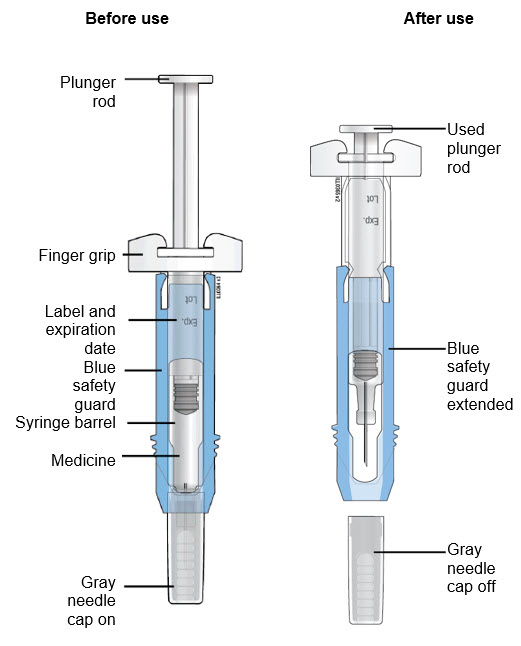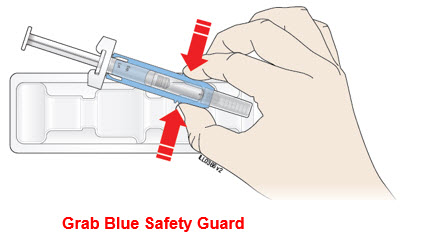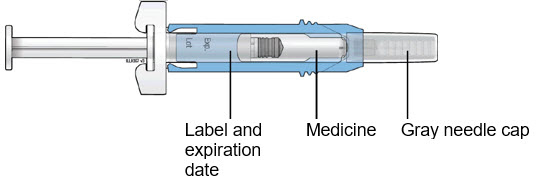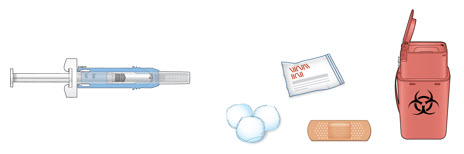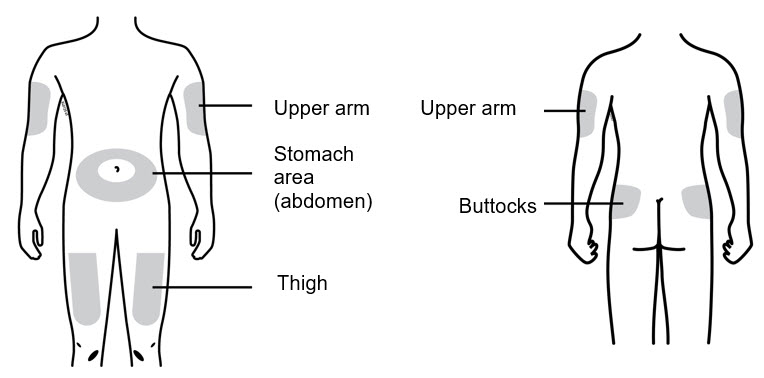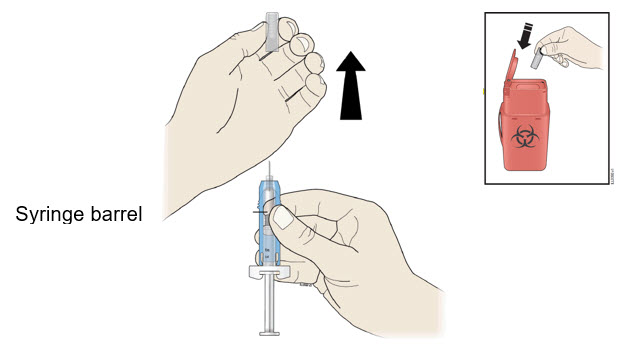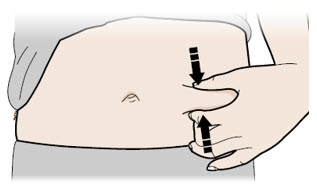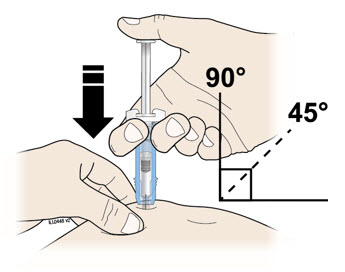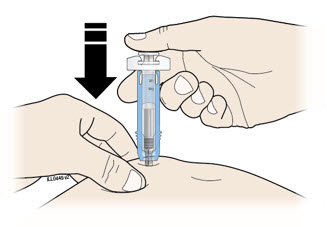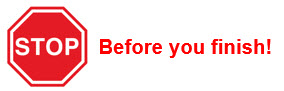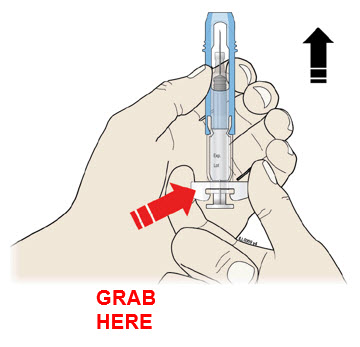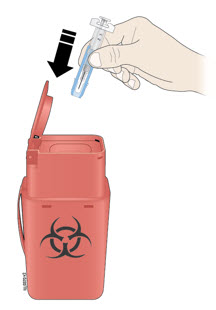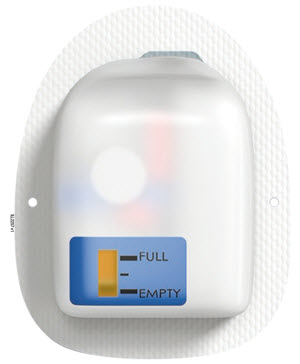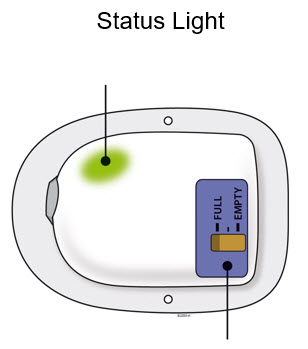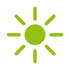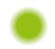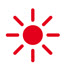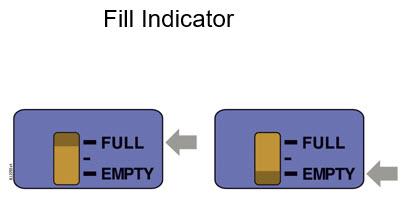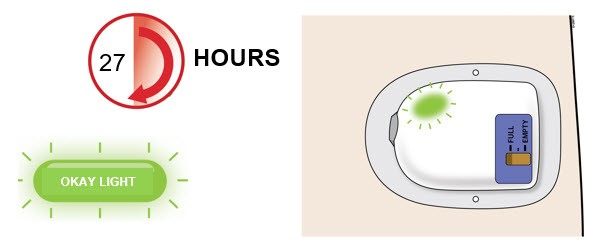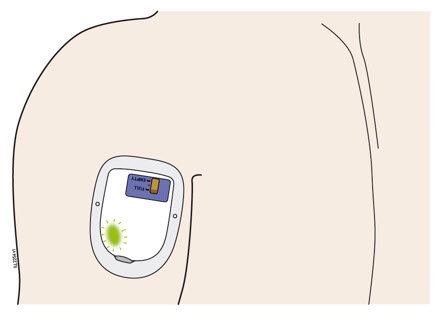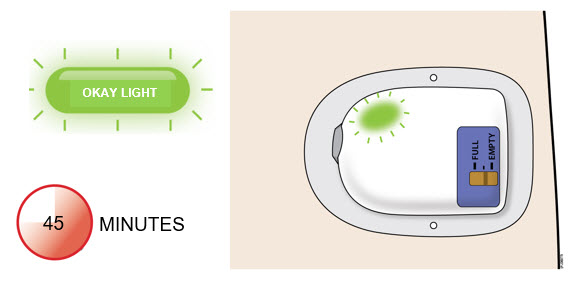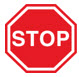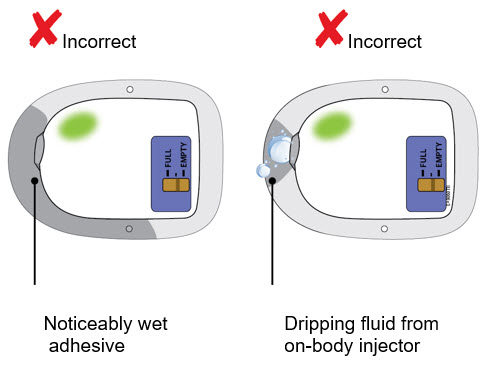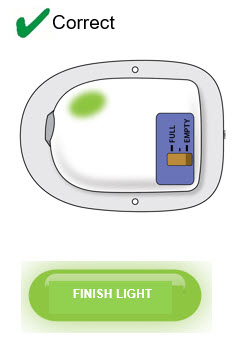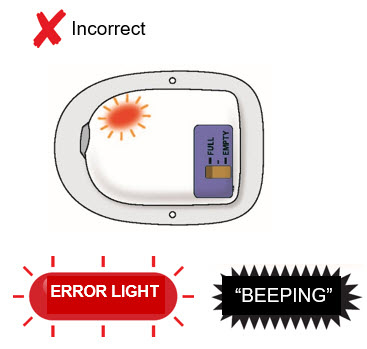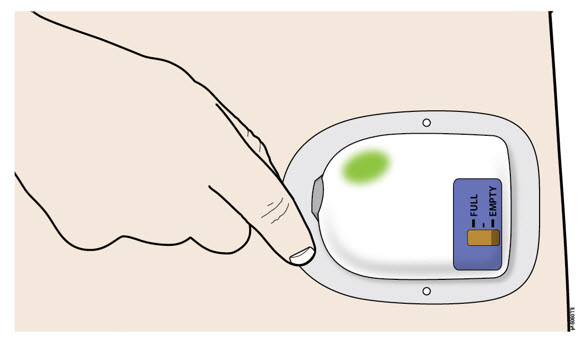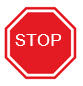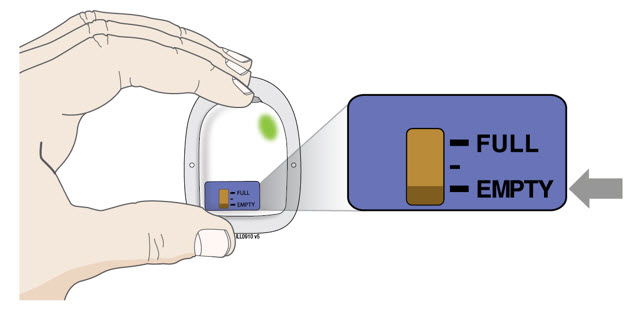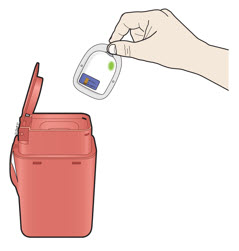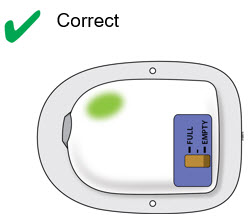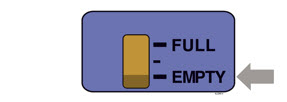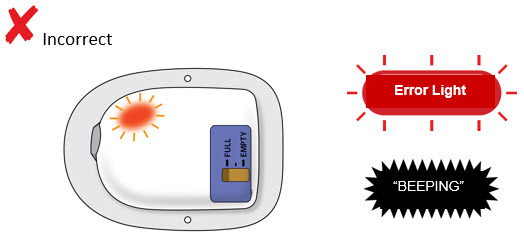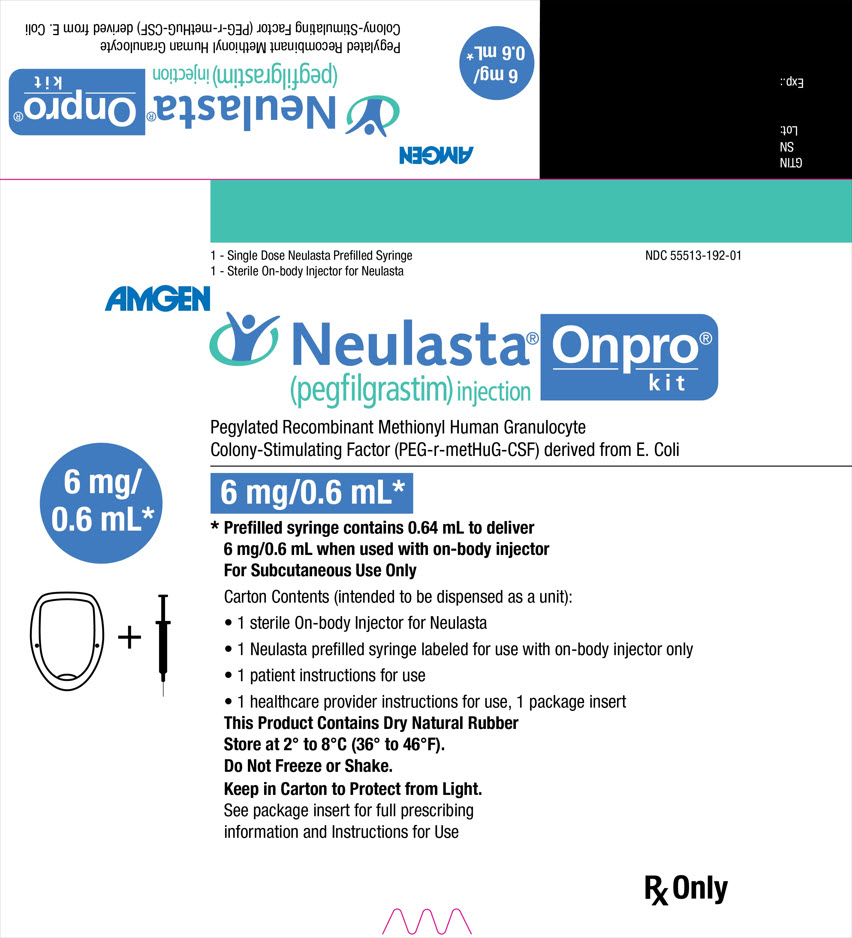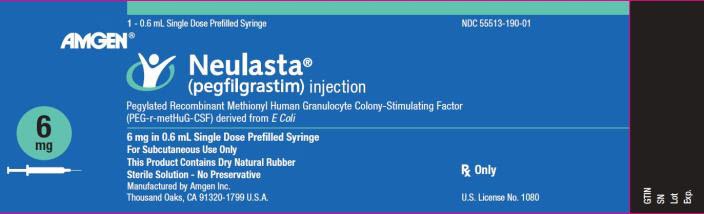 DRUG LABEL: Neulasta
NDC: 55513-192 | Form: KIT | Route: SUBCUTANEOUS
Manufacturer: Amgen Inc
Category: prescription | Type: HUMAN PRESCRIPTION DRUG LABEL
Date: 20250414

ACTIVE INGREDIENTS: PEGFILGRASTIM 6 mg/0.6 mL
INACTIVE INGREDIENTS: ACETIC ACID 0.35 mg/0.6 mL; POLYSORBATE 20 0.02 mg/0.6 mL; SODIUM HYDROXIDE; SORBITOL 30 mg/0.6 mL; WATER

HIGHLIGHTS OF PRESCRIBING INFORMATION

These highlights do not include all the information needed to use NEULASTA safely and effectively. See full prescribing information for NEULASTA.
NEULASTA® (pegfilgrastim) injection, for subcutaneous use
Initial U.S. Approval: 2002

RECENT MAJOR CHANGES

Warnings and Precautions, Thrombocytopenia (5.8) | 01/2021
Warnings and Precautions, Myelodysplastic Syndrome (MDS) and Acute Myeloid Leukemia (AML) (5.11) | 01/2021

1 INDICATIONS AND USAGE

Neulasta is a leukocyte growth factor indicated to

- Decrease the incidence of infection, as manifested by febrile neutropenia, in patients with non-myeloid malignancies receiving myelosuppressive anti-cancer drugs associated with a clinically significant incidence of febrile neutropenia. (1.1)
- Increase survival in patients acutely exposed to myelosuppressive doses of radiation (Hematopoietic Subsyndrome of Acute Radiation Syndrome). (1.2)

Limitations of Use

Neulasta is not indicated for the mobilization of peripheral blood progenitor cells for hematopoietic stem cell transplantation.

2 DOSAGE AND ADMINISTRATION

- Patients with cancer receiving myelosuppressive chemotherapy
  - 6 mg administered subcutaneously once per chemotherapy cycle. (2.1)
  - Do not administer between 14 days before and 24 hours after administration of cytotoxic chemotherapy. (2.1)
  - Use weight based dosing for pediatric patients weighing less than 45 kg; refer to Table 1. (2.3)
- Patients acutely exposed to myelosuppressive doses of radiation
  - Two doses, 6 mg each, administered subcutaneously one week apart. Administer the first dose as soon as possible after suspected or confirmed exposure to myelosuppressive doses of radiation, and a second dose one week after. (2.2)
  - Use weight based dosing for pediatric patients weighing less than 45 kg; refer to Table 1. (2.3)

3 DOSAGE FORMS AND STRENGTHS

- Injection: 6 mg/0.6 mL solution in a single-dose prefilled syringe for manual use only. (3)
- Injection: 6 mg/0.6 mL solution in a single-dose prefilled syringe co-packaged with the on-body injector for Neulasta. (3)

4 CONTRAINDICATIONS

Patients with a history of serious allergic reactions to human granulocyte colony-stimulating factors such as pegfilgrastim or filgrastim. (4)

5 WARNINGS AND PRECAUTIONS

- Fatal splenic rupture: Evaluate patients who report left upper abdominal or shoulder pain for an enlarged spleen or splenic rupture. (5.1)
- Acute respiratory distress syndrome (ARDS): Evaluate patients who develop fever, lung infiltrates, or respiratory distress. Discontinue Neulasta in patients with ARDS. (5.2)
- Serious allergic reactions, including anaphylaxis: Permanently discontinue Neulasta in patients with serious allergic reactions. (5.3)
- The on-body injector for Neulasta uses acrylic adhesive. For patients who have reactions to acrylic adhesives, use of this product may result in a significant reaction. (5.4)
- Fatal sickle cell crises: Discontinue Neulasta if sickle cell crisis occurs. (5.5)
- Glomerulonephritis: Evaluate and consider dose-reduction or interruption of Neulasta if causality is likely. (5.6)
- Thrombocytopenia: Monitor platelet counts. (5.8)
- Myelodysplastic Syndrome (MDS) and Acute Myeloid Leukemia (AML): Monitor patients with breast and lung cancer using Neulasta in conjunction with chemotherapy and/or radiotherapy for signs and symptoms of MDS/AML. (5.11)
- Potential device failures: Instruct patients to notify their healthcare provider if they suspect the on-body injector may not have performed as intended. (5.12)

6 ADVERSE REACTIONS

Most common adverse reactions (≥ 5% difference in incidence compared to placebo) are bone pain and pain in extremity. (6.1)

To report SUSPECTED ADVERSE REACTIONS, contact Amgen Inc. at 1-800-77-AMGEN (1-800-772-6436) or FDA at 1-800-FDA-1088 or www.fda.gov/medwatch.

FULL PRESCRIBING INFORMATION

1 INDICATIONS AND USAGE

1.1 Patients with Cancer Receiving Myelosuppressive Chemotherapy

Neulasta is indicated to decrease the incidence of infection, as manifested by febrile neutropenia, in patients with non-myeloid malignancies receiving myelosuppressive anti-cancer drugs associated with a clinically significant incidence of febrile neutropenia [see Clinical Studies (14.1)].

Limitations of Use

Neulasta is not indicated for the mobilization of peripheral blood progenitor cells for hematopoietic stem cell transplantation.

1.2 Patients with Hematopoietic Subsyndrome of Acute Radiation Syndrome

Neulasta is indicated to increase survival in patients acutely exposed to myelosuppressive doses of radiation [see Dosage and Administration (2.2) and Clinical Studies (14.2)].

2 DOSAGE AND ADMINISTRATION

2.1 Patients with Cancer Receiving Myelosuppressive Chemotherapy

The recommended dosage of Neulasta is a single subcutaneous injection of 6 mg administered once per chemotherapy cycle. For dosing in pediatric patients weighing less than 45 kg, refer to Table 1. Do not administer Neulasta between 14 days before and 24 hours after administration of cytotoxic chemotherapy.

2.2 Patients with Hematopoietic Subsyndrome of Acute Radiation Syndrome

The recommended dose of Neulasta is two doses, 6 mg each, administered subcutaneously one week apart. For dosing in pediatric patients weighing less than 45 kg, refer to Table 1. Administer the first dose as soon as possible after suspected or confirmed exposure to radiation levels greater than 2 gray (Gy). Administer the second dose one week after the first dose.

Obtain a baseline complete blood count (CBC). Do not delay administration of Neulasta if a CBC is not readily available. Estimate a patient's absorbed radiation dose (i.e., level of radiation exposure) based on information from public health authorities, biodosimetry if available, or clinical findings such as time to onset of vomiting or lymphocyte depletion kinetics.

2.3 Administration

Neulasta is administered subcutaneously via a single-dose prefilled syringe for manual use or for use with the on-body injector (OBI) for Neulasta, which is co-packaged with a single-dose prefilled syringe. Use of the OBI for Neulasta is not recommended for patients with Hematopoietic Subsyndrome of Acute Radiation Syndrome. Use of the OBI for Neulasta has not been studied in pediatric patients.

Prior to use‚ remove the carton from the refrigerator and allow the Neulasta prefilled syringe to reach room temperature for a minimum of 30 minutes. Discard any prefilled syringe left at room temperature for greater than 48 hours.

Parenteral drug products should be inspected visually for particulate matter and discoloration prior to administration, whenever solution and container permit. Do not administer Neulasta if discoloration or particulates are observed.

The needle cap on the prefilled syringes contains dry natural rubber (derived from latex); persons with latex allergies should not administer these products.

Pediatric Patients weighing less than 45 kg

The Neulasta prefilled syringe is not designed to allow for direct administration of doses less than 0.6 mL (6 mg). The syringe does not bear graduation marks, which are necessary to accurately measure doses of Neulasta less than 0.6 mL (6 mg) for direct administration to patients. Thus, the direct administration to patients requiring dosing of less than 0.6 mL (6 mg) is not recommended due to the potential for dosing errors. Refer to Table 1.

Table 1. Dosing of Neulasta for pediatric patients weighing less than 45 kg
Body Weight | Neulasta Dose | Volume to Administer
Less than 10 kg [For pediatric patients weighing less than 10 kg, administer 0.1 mg/kg (0.01 mL/kg) of Neulasta.] | See below | See below
10 - 20 kg | 1.5 mg | 0.15 mL
21 - 30 kg | 2.5 mg | 0.25 mL
31 - 44 kg | 4 mg | 0.4 mL

2.4 Special Healthcare Provider Instructions for the On-body Injector for Neulasta

A healthcare provider must fill the on-body injector (OBI) with Neulasta using the prefilled syringe and then apply the OBI for Neulasta to the patient's skin (abdomen or back of arm). The back of the arm may only be used if there is a caregiver available to monitor the status of the OBI for Neulasta. Approximately 27 hours after the OBI for Neulasta is applied to the patient's skin, Neulasta will be delivered over approximately 45 minutes. A healthcare provider may initiate administration with the OBI for Neulasta on the same day as the administration of cytotoxic chemotherapy, as long as the OBI for Neulasta delivers Neulasta no less than 24 hours after administration of cytotoxic chemotherapy.

The prefilled syringe co-packaged in Neulasta Onpro® kit must only be used with the OBI for Neulasta. The prefilled syringe contains additional solution to compensate for liquid loss during delivery through the OBI for Neulasta. If the prefilled syringe co-packaged in Neulasta Onpro kit is used for manual subcutaneous injection, the patient will receive an overdose. If the single-dose prefilled syringe for manual use is used with the OBI for Neulasta, the patient may receive less than the recommended dose.

Do not use the OBI for Neulasta to deliver any other drug product except the Neulasta prefilled syringe co-packaged with the OBI for Neulasta.

The OBI for Neulasta should be applied to intact, non-irritated skin on the arm or abdomen.

A missed dose could occur due to an OBI for Neulasta failure or leakage. If the patient misses a dose, a new dose should be administered by single-dose prefilled syringe for manual use, as soon as possible after detection.

Refer to the Healthcare Provider Instructions for Use for the OBI for Neulasta for full administration information.

2.5 Advice to Give to Patients Regarding Administration via the On-body Injector for Neulasta

Advise patients to avoid activities such as traveling, driving, or operating heavy machinery during hours 26-29 following application of the on-body injector (OBI) for Neulasta (this includes the 45-minute delivery period plus an hour post-delivery). Patients should have a caregiver nearby for the first use.

Refer the patient to the dose delivery information written on the Patient Instructions for Use. Provide training to patients to ensure they understand when the dose delivery of Neulasta will begin and how to monitor the OBI for Neulasta for completed delivery. Ensure patients understand how to identify signs of malfunction of OBI for Neulasta [see Warnings and Precautions (5.12) and Patient Counseling Information (17)]. Instruct patients using the OBI to notify their healthcare professional immediately in order to determine the need for a replacement dose of Neulasta if they suspect that the device may not have performed as intended [see Warnings and Precautions (5.12)].

3 DOSAGE FORMS AND STRENGTHS

Neulasta is a clear, colorless, preservative-free solution available as:

- Injection: 6 mg/0.6 mL in a single-dose prefilled syringe for manual use only.
- Injection: 6 mg/0.6 mL in a single-dose prefilled syringe co-packaged with the on-body injector (OBI) for Neulasta (Neulasta Onpro kit).

4 CONTRAINDICATIONS

Neulasta is contraindicated in patients with a history of serious allergic reactions to pegfilgrastim or filgrastim. Reactions have included anaphylaxis [see Warnings and Precautions (5.3)].

5 WARNINGS AND PRECAUTIONS

5.1 Splenic Rupture

Splenic rupture, including fatal cases, can occur following the administration of Neulasta. Evaluate for an enlarged spleen or splenic rupture in patients who report left upper abdominal or shoulder pain after receiving Neulasta.

5.2 Acute Respiratory Distress Syndrome

Acute respiratory distress syndrome (ARDS) can occur in patients receiving Neulasta. Evaluate patients who develop fever and lung infiltrates or respiratory distress after receiving Neulasta, for ARDS. Discontinue Neulasta in patients with ARDS.

5.3 Serious Allergic Reactions

Serious allergic reactions, including anaphylaxis, can occur in patients receiving Neulasta. The majority of reported events occurred upon initial exposure. Allergic reactions, including anaphylaxis, can recur within days after the discontinuation of initial anti-allergic treatment. Permanently discontinue Neulasta in patients with serious allergic reactions. Do not administer Neulasta to patients with a history of serious allergic reactions to pegfilgrastim or filgrastim.

5.4 Allergies to Acrylics

The on-body injector (OBI) for Neulasta uses acrylic adhesive. For patients who have reactions to acrylic adhesives, use of this product may result in a significant reaction.

5.5 Use in Patients with Sickle Cell Disorders

Severe and sometimes fatal sickle cell crises can occur in patients with sickle cell disorders receiving pegfilgrastim products. Discontinue Neulasta if sickle cell crisis occurs.

5.6 Glomerulonephritis

Glomerulonephritis has occurred in patients receiving Neulasta. The diagnoses were based upon azotemia, hematuria (microscopic and macroscopic), proteinuria, and renal biopsy. Generally, events of glomerulonephritis resolved after dose-reduction or discontinuation of Neulasta. If glomerulonephritis is suspected, evaluate for cause. If causality is likely, consider dose-reduction or interruption of Neulasta.

5.7 Leukocytosis

White blood cell (WBC) counts of 100 × 10^9/L or greater have been observed in patients receiving pegfilgrastim. Monitoring of complete blood count (CBC) during pegfilgrastim therapy is recommended.

5.8 Thrombocytopenia

Thrombocytopenia has been reported in patients receiving pegfilgrastim. Monitor platelet counts.

5.9 Capillary Leak Syndrome

Capillary leak syndrome has been reported after G-CSF administration, including Neulasta, and is characterized by hypotension, hypoalbuminemia, edema and hemoconcentration. Episodes vary in frequency, severity and may be life-threatening if treatment is delayed. Patients who develop symptoms of capillary leak syndrome should be closely monitored and receive standard symptomatic treatment, which may include a need for intensive care.

5.10 Potential for Tumor Growth Stimulatory Effects on Malignant Cells

The granulocyte colony-stimulating factor (G-CSF) receptor through which pegfilgrastim and filgrastim act has been found on tumor cell lines. The possibility that pegfilgrastim acts as a growth factor for any tumor type, including myeloid malignancies and myelodysplasia, diseases for which pegfilgrastim is not approved, cannot be excluded.

5.11 Myelodysplastic Syndrome (MDS) and Acute Myeloid Leukemia (AML) in Patients with Breast and Lung Cancer

MDS and AML have been associated with the use of Neulasta in conjunction with chemotherapy and/or radiotherapy in patients with breast and lung cancer. Monitor patients for signs and symptoms of MDS/AML in these settings.

5.12 Potential Device Failures

Missed or partial doses have been reported in patients receiving Neulasta via the on-body injector (OBI) due to the device not performing as intended. In the event of a missed or partial dose, patients may be at increased risk of events such as neutropenia, febrile neutropenia and/or infection than if the dose had been correctly delivered. Instruct patients using the OBI to notify their healthcare professional immediately in order to determine the need for a replacement dose of Neulasta if they suspect that the device may not have performed as intended.

5.13 Aortitis

Aortitis has been reported in patients receiving Neulasta. It may occur as early as the first week after start of therapy. Manifestations may include generalized signs and symptoms such as fever, abdominal pain, malaise, back pain, and increased inflammatory markers (e.g., c-reactive protein and white blood cell count). Consider aortitis in patients who develop these signs and symptoms without known etiology. Discontinue Neulasta if aortitis is suspected.

5.14 Nuclear Imaging

Increased hematopoietic activity of the bone marrow in response to growth factor therapy has been associated with transient positive bone imaging changes. This should be considered when interpreting bone imaging results.

6 ADVERSE REACTIONS

The following clinically significant adverse reactions are discussed in greater detail in other sections of the labeling:

- Splenic Rupture [see Warnings and Precautions (5.1)]
- Acute Respiratory Distress Syndrome [see Warnings and Precautions (5.2)]
- Serious Allergic Reactions [see Warnings and Precautions (5.3)]
- Allergies to Acrylics [see Warnings and Precautions (5.4)]
- Use in Patients with Sickle Cell Disorders [see Warnings and Precautions (5.5)]
- Glomerulonephritis [see Warnings and Precautions (5.6)]
- Leukocytosis [see Warnings and Precautions (5.7)]
- Thrombocytopenia [see Warnings and Precautions (5.8)]
- Capillary Leak Syndrome [see Warnings and Precautions (5.9)]
- Potential for Tumor Growth Stimulatory Effects on Malignant Cells [see Warnings and Precautions (5.10)]
- Myelodysplastic syndrome [see Warnings and Precautions (5.11)]
- Acute myeloid leukemia [see Warnings and Precautions (5.11)]
- Aortitis [see Warnings and Precautions (5.13)]

6.1 Clinical Trials Experience

Because clinical trials are conducted under widely varying conditions, adverse reaction rates observed in the clinical trials of a drug cannot be directly compared with rates in the clinical trials of another drug and may not reflect the rates observed in clinical practice.

Neulasta clinical trials safety data are based upon 932 patients receiving Neulasta in seven randomized clinical trials. The population was 21 to 88 years of age and 92% female. The ethnicity was 75% Caucasian, 18% Hispanic, 5% Black, and 1% Asian. Patients with breast (n = 823), lung and thoracic tumors (n = 53) and lymphoma (n = 56) received Neulasta after nonmyeloablative cytotoxic chemotherapy. Most patients received a single 100 mcg/kg (n = 259) or a single 6 mg (n = 546) dose per chemotherapy cycle over 4 cycles.

The following adverse reaction data in Table 2 are from a randomized, double-blind, placebo-controlled study in patients with metastatic or non-metastatic breast cancer receiving docetaxel 100 mg/m^2 every 21 days (Study 3). A total of 928 patients were randomized to receive either 6 mg Neulasta (n = 467) or placebo (n = 461). The patients were 21 to 88 years of age and 99% female. The ethnicity was 66% Caucasian, 31% Hispanic, 2% Black, and < 1% Asian, Native American, or other.

The most common adverse reactions occurring in ≥ 5% of patients and with a between-group difference of ≥ 5% higher in the pegfilgrastim arm in placebo-controlled clinical trials are bone pain and pain in extremity.

Table 2. Adverse Reactions with ≥ 5% Higher Incidence in Neulasta Patients Compared to Placebo in Study 3
Body System Adverse Reaction | Placebo (N = 461) | Neulasta 6 mg SC on Day 2 (N = 467)
Musculoskeletal and connective tissue disorders
Bone pain | 26% | 31%
Pain in extremity | 4% | 9%

Leukocytosis

In clinical studies, leukocytosis (WBC counts > 100 × 10^9/L) was observed in less than 1% of 932 patients with non-myeloid malignancies receiving Neulasta. No complications attributable to leukocytosis were reported in clinical studies.

6.2 Immunogenicity

As with all therapeutic proteins, there is a potential for immunogenicity. The detection of antibody formation is highly dependent on the sensitivity and specificity of the assay. Additionally, the observed incidence of antibody (including neutralizing antibody) positivity in an assay may be influenced by several factors, including assay methodology, sample handling, timing of sample collection, concomitant medications, and underlying disease. For these reasons, comparison of the incidence of antibodies to pegfilgrastim in the studies described below with the incidence of antibodies in other studies or to other products may be misleading.

Binding antibodies to pegfilgrastim were detected using a BIAcore assay. The approximate limit of detection for this assay is 500 ng/mL. Pre-existing binding antibodies were detected in approximately 6% (51/849) of patients with metastatic breast cancer. Four of 521 pegfilgrastim-treated subjects who were negative at baseline developed binding antibodies to pegfilgrastim following treatment. None of these 4 patients had evidence of neutralizing antibodies detected using a cell-based bioassay.

6.3 Postmarketing Experience

The following adverse reactions have been identified during post approval use of Neulasta. Because these reactions are reported voluntarily from a population of uncertain size, it is not always possible to reliably estimate their frequency or establish a causal relationship to drug exposure.

- Splenic rupture and splenomegaly (enlarged spleen) [see Warnings and Precautions (5.1)]
- Acute respiratory distress syndrome (ARDS) [see Warnings and Precautions (5.2)]
- Allergic reactions/hypersensitivity, including anaphylaxis, skin rash, urticaria, generalized erythema, and flushing [see Warnings and Precautions (5.3)]
- Sickle cell crisis [see Warnings and Precautions (5.5)]
- Glomerulonephritis [see Warnings and Precautions (5.6)]
- Leukocytosis [see Warnings and Precautions (5.7)]
- Thrombocytopenia [see Warnings and Precautions (5.8)]
- Capillary Leak Syndrome [see Warnings and Precautions (5.9)]
- Injection site reactions
- Sweet's syndrome (acute febrile neutrophilic dermatosis), cutaneous vasculitis
- Application site reactions (including events such as application site hemorrhage, application site pain, application site discomfort, application site bruise, and application site erythema) have been reported with the use of the on-body injector for Neulasta.
- Contact dermatitis and local skin reactions such as rash, pruritus, and urticaria have been reported with the use of the on-body injector for Neulasta, possibly indicating a hypersensitivity reaction to the adhesive.
- Myelodysplastic syndrome (MDS) and acute myeloid leukemia (AML) in patients with breast and lung cancer receiving chemotherapy and/or radiotherapy [see Warnings and Precautions (5.11)]
- Aortitis [see Warnings and Precautions (5.13)]
- Alveolar hemorrhage

8 USE IN SPECIFIC POPULATIONS

8.1 Pregnancy

Risk Summary

Although available data with Neulasta use in pregnant women are insufficient to establish whether there is a drug associated risk of major birth defects, miscarriage, or adverse maternal or fetal outcomes, there are available data from published studies in pregnant women exposed to filgrastim products. These studies have not established an association of filgrastim product use during pregnancy with major birth defects, miscarriage, or adverse maternal or fetal outcomes.

In animal studies, no evidence of reproductive/developmental toxicity occurred in the offspring of pregnant rats that received cumulative doses of pegfilgrastim approximately 10 times the recommended human dose (based on body surface area). In pregnant rabbits, increased embryolethality and spontaneous abortions occurred at 4 times the maximum recommended human dose simultaneously with signs of maternal toxicity (see Data).

The estimated background risk of major birth defects and miscarriage for the indicated population is unknown. All pregnancies have a background risk of birth defect, loss, or other adverse outcomes. In the U.S. general population, the estimated background risks of major birth defects and miscarriage in clinically recognized pregnancies is 2-4% and 15-20%, respectively.

Data

Animal Data

Pregnant rabbits were dosed with pegfilgrastim subcutaneously every other day during the period of organogenesis. At cumulative doses ranging from the approximate human dose to approximately 4 times the recommended human dose (based on body surface area), the treated rabbits exhibited decreased maternal food consumption, maternal weight loss, as well as reduced fetal body weights and delayed ossification of the fetal skull; however, no structural anomalies were observed in the offspring from either study. Increased incidences of post-implantation losses and spontaneous abortions (more than half the pregnancies) were observed at cumulative doses approximately 4 times the recommended human dose, which were not seen when pregnant rabbits were exposed to the recommended human dose.

Three studies were conducted in pregnant rats dosed with pegfilgrastim at cumulative doses up to approximately 10 times the recommended human dose at the following stages of gestation: during the period of organogenesis, from mating through the first half of pregnancy, and from the first trimester through delivery and lactation. No evidence of fetal loss or structural malformations was observed in any study. Cumulative doses equivalent to approximately 3 and 10 times the recommended human dose resulted in transient evidence of wavy ribs in fetuses of treated mothers (detected at the end of gestation but no longer present in pups evaluated at the end of lactation).

8.2 Lactation

Risk Summary

There are no data on the presence of pegfilgrastim in human milk, the effects on the breastfed child, or the effects on milk production. Other filgrastim products are secreted poorly into breast milk, and filgrastim products are not absorbed orally by neonates. The developmental and health benefits of breastfeeding should be considered along with the mother's clinical need for Neulasta and any potential adverse effects on the breastfed child from Neulasta or from the underlying maternal condition.

8.4 Pediatric Use

The safety and effectiveness of Neulasta have been established in pediatric patients. No overall differences in safety were identified between adult and pediatric patients based on postmarketing surveillance and review of the scientific literature.

Use of Neulasta in pediatric patients for chemotherapy-induced neutropenia is based on adequate and well-controlled studies in adults with additional pharmacokinetic and safety data in pediatric patients with sarcoma [see Clinical Pharmacology (12.3) and Clinical Studies (14.1)].

The use of Neulasta to increase survival in pediatric patients acutely exposed to myelosuppressive doses of radiation is based on efficacy studies conducted in animals and clinical data supporting the use of Neulasta in patients with cancer receiving myelosuppressive chemotherapy. Efficacy studies of Neulasta could not be conducted in humans with acute radiation syndrome for ethical and feasibility reasons. Results from population modeling and simulation indicate that two doses of Neulasta (Table 1), administered one week apart provide pediatric patients with exposures comparable to that in adults receiving two 6 mg doses one week apart [see Dosage and Administration (2.3), Clinical Pharmacology (12.3) and Clinical Studies (14.2)].

8.5 Geriatric Use

Of the 932 patients with cancer who received Neulasta in clinical studies, 139 (15%) were aged 65 and over, and 18 (2%) were aged 75 and over. No overall differences in safety or effectiveness were observed between patients aged 65 and older and younger patients.

10 OVERDOSAGE

Overdosage of Neulasta may result in leukocytosis and bone pain. Events of edema, dyspnea, and pleural effusion have been reported in a single patient who administered Neulasta on 8 consecutive days in error. In the event of overdose, the patient should be monitored for adverse reactions [see Adverse Reactions (6)].

11 DESCRIPTION

Pegfilgrastim is a covalent conjugate of recombinant methionyl human G-CSF (filgrastim) and monomethoxypolyethylene glycol. Filgrastim is a water-soluble 175 amino acid protein with a molecular weight of approximately 19 kilodaltons (kD). Filgrastim is obtained from the bacterial fermentation of a strain of E coli transformed with a genetically engineered plasmid containing the human G-CSF gene. To produce pegfilgrastim, a 20 kD monomethoxypolyethylene glycol molecule is covalently bound to the N-terminal methionyl residue of filgrastim. The average molecular weight of pegfilgrastim is approximately 39 kD.

Neulasta is provided in two presentations:

- Neulasta for manual subcutaneous injection is supplied in 0.6 mL prefilled syringes. The prefilled syringe does not bear graduation marks and is designed to deliver the entire contents of the syringe (6 mg/0.6 mL).
- On-body injector (OBI) for Neulasta is supplied with a prefilled syringe containing 0.64 mL of Neulasta in solution that delivers 0.6 mL of Neulasta in solution when used with the OBI for Neulasta. The syringe does not bear graduation marks and is only to be used with the OBI for Neulasta.

The delivered 0.6 mL dose from either the prefilled syringe for manual subcutaneous injection or the OBI for Neulasta contains 6 mg pegfilgrastim (based on protein weight) in a sterile, clear, colorless, preservative-free solution (pH 4.0) containing acetate (0.35 mg), polysorbate 20 (0.02 mg), sodium (0.02 mg), and sorbitol (30 mg) in Water for Injection, USP.

12 CLINICAL PHARMACOLOGY

12.1 Mechanism of Action

Pegfilgrastim is a colony-stimulating factor that acts on hematopoietic cells by binding to specific cell surface receptors, thereby stimulating proliferation, differentiation, commitment, and end cell functional activation.

12.2 Pharmacodynamics

Animal data and clinical data in humans suggest a correlation between pegfilgrastim exposure and the duration of severe neutropenia as a predictor of efficacy. Selection of the dosing regimen of Neulasta is based on reducing the duration of severe neutropenia.

12.3 Pharmacokinetics

The pharmacokinetics of pegfilgrastim was studied in 379 patients with cancer. The pharmacokinetics of pegfilgrastim was nonlinear, and clearance decreased with increases in dose. Neutrophil receptor binding is an important component of the clearance of pegfilgrastim, and serum clearance is directly related to the number of neutrophils. In addition to numbers of neutrophils, body weight appeared to be a factor. Patients with higher body weights experienced higher systemic exposure to pegfilgrastim after receiving a dose normalized for body weight. A large variability in the pharmacokinetics of pegfilgrastim was observed. The half-life of Neulasta ranged from 15 to 80 hours after subcutaneous injection. In healthy volunteers, the pharmacokinetics of pegfilgrastim were comparable when delivered subcutaneously via a manual prefilled syringe versus via the on-body injector (OBI) for Neulasta.

Specific Populations

No gender-related differences were observed in the pharmacokinetics of pegfilgrastim, and no differences were observed in the pharmacokinetics of geriatric patients (≥ 65 years of age) compared with younger patients (< 65 years of age) [see Use in Specific Populations (8.5)].

Renal Impairment

In a study of 30 subjects with varying degrees of renal dysfunction, including end stage renal disease, renal dysfunction had no effect on the pharmacokinetics of pegfilgrastim.

Pediatric Patients with Cancer Receiving Myelosuppressive Chemotherapy

The pharmacokinetics and safety of pegfilgrastim were studied in 37 pediatric patients with sarcoma in Study 4 [see Clinical Studies (14.1)]. The mean (± standard deviation [SD]) systemic exposure (AUC0-inf) of Neulasta after subcutaneous administration at 100 mcg/kg was 47.9 (± 22.5) mcg∙hr/mL in the youngest age group (0 to 5 years, n = 11), 22.0 (± 13.1) mcg∙hr/mL in the 6 to 11 years age group (n = 10), and 29.3 (± 23.2) mcg∙hr/mL in the 12 to 21 years age group (n = 13). The terminal elimination half-lives of the corresponding age groups were 30.1 (± 38.2) hours, 20.2 (± 11.3) hours, and 21.2 (± 16.0) hours, respectively.

Patients Acutely Exposed to Myelosuppressive Doses of Radiation

The pharmacokinetics of pegfilgrastim is not available in patients acutely exposed to myelosuppressive doses of radiation. Based on limited pharmacokinetic data in irradiated non-human primates, the area under the concentration-time curve (AUC), reflecting the exposure to pegfilgrastim in non-human primates following a 300 mcg/kg dose of Neulasta, appears to be greater than in humans receiving a 6 mg dose. Results from population modeling and simulation indicate that two 6 mg doses of Neulasta administered one week apart in adults result in clinically relevant effects on duration of grade 3 and 4 neutropenia. In addition, weight based dosing in pediatric patients weighing less than 45 kg [see Dosage and Administration, Section 2.3, Table 1] provides exposures comparable to those in adults receiving two 6 mg doses one week apart.

13 NONCLINICAL TOXICOLOGY

13.1 Carcinogenesis, Mutagenesis, Impairment of Fertility

No carcinogenicity or mutagenesis studies have been performed with pegfilgrastim.

Pegfilgrastim did not affect reproductive performance or fertility in male or female rats at cumulative weekly doses approximately 6 to 9 times higher than the recommended human dose (based on body surface area).

14 CLINICAL STUDIES

14.1 Patients with Cancer Receiving Myelosuppressive Chemotherapy

Neulasta was evaluated in three randomized, double-blind, controlled studies. Studies 1 and 2 were active-controlled studies that employed doxorubicin 60 mg/m^2 and docetaxel 75 mg/m^2 administered every 21 days for up to 4 cycles for the treatment of metastatic breast cancer. Study 1 investigated the utility of a fixed dose of Neulasta. Study 2 employed a weight-adjusted dose. In the absence of growth factor support, similar chemotherapy regimens have been reported to result in a 100% incidence of severe neutropenia (ANC < 0.5 × 10^9/L) with a mean duration of 5 to 7 days and a 30% to 40% incidence of febrile neutropenia. Based on the correlation between the duration of severe neutropenia and the incidence of febrile neutropenia found in studies with filgrastim, duration of severe neutropenia was chosen as the primary endpoint in both studies, and the efficacy of Neulasta was demonstrated by establishing comparability to filgrastim-treated patients in the mean days of severe neutropenia.

In Study 1, 157 patients were randomized to receive a single subcutaneous injection of Neulasta (6 mg) on day 2 of each chemotherapy cycle or daily subcutaneous filgrastim (5 mcg/kg/day) beginning on day 2 of each chemotherapy cycle. In Study 2, 310 patients were randomized to receive a single subcutaneous injection of Neulasta (100 mcg/kg) on day 2 or daily subcutaneous filgrastim (5 mcg/kg/day) beginning on day 2 of each chemotherapy cycle.

Both studies met the major efficacy outcome measure of demonstrating that the mean days of severe neutropenia of Neulasta-treated patients did not exceed that of filgrastim-treated patients by more than 1 day in cycle 1 of chemotherapy. The mean days of cycle 1 severe neutropenia in Study 1 were 1.8 days in the Neulasta arm compared to 1.6 days in the filgrastim arm [difference in means 0.2 (95% CI - 0.2, 0.6)] and in Study 2 were 1.7 days in the Neulasta arm compared to 1.6 days in the filgrastim arm [difference in means 0.1 (95% CI - 0.2, 0.4)].

A secondary endpoint in both studies was days of severe neutropenia in cycles 2 through 4 with results similar to those for cycle 1.

Study 3 was a randomized, double-blind, placebo-controlled study that employed docetaxel 100 mg/m^2 administered every 21 days for up to 4 cycles for the treatment of metastatic or non-metastatic breast cancer. In this study, 928 patients were randomized to receive a single subcutaneous injection of Neulasta (6 mg) or placebo on day 2 of each chemotherapy cycle. Study 3 met the major trial outcome measure of demonstrating that the incidence of febrile neutropenia (defined as temperature ≥ 38.2°C and ANC ≤ 0.5 × 10^9/L) was lower for Neulasta-treated patients as compared to placebo-treated patients (1% versus 17%, respectively, p < 0.001). The incidence of hospitalizations (1% versus 14%) and IV anti-infective use (2% versus 10%) for the treatment of febrile neutropenia was also lower in the Neulasta-treated patients compared to the placebo-treated patients.

Study 4 was a multicenter, randomized, open-label study to evaluate the efficacy, safety, and pharmacokinetics [see Clinical Pharmacology (12.3)] of Neulasta in pediatric and young adult patients with sarcoma. Patients with sarcoma receiving chemotherapy age 0 to 21 years were eligible. Patients were randomized to receive subcutaneous Neulasta as a single-dose of 100 mcg/kg (n = 37) or subcutaneous filgrastim at a dose 5 mcg/kg/day (n = 6) following myelosuppressive chemotherapy. Recovery of neutrophil counts was similar in the Neulasta and filgrastim groups. The most common adverse reaction reported was bone pain.

14.2 Patients with Hematopoietic Subsyndrome of Acute Radiation Syndrome

Efficacy studies of Neulasta could not be conducted in humans with acute radiation syndrome for ethical and feasibility reasons. Approval of this indication was based on efficacy studies conducted in animals and data supporting Neulasta's effect on severe neutropenia in patients with cancer receiving myelosuppressive chemotherapy [see Dosage and Administration (2.1)].

The recommended dose of Neulasta is two doses, 6 mg each, administered one week apart for humans exposed to myelosuppressive doses of radiation. For pediatric patients weighing less than 45 kg, dosing of Neulasta is weight based and is provided in Table 1 [see Dosage and Administration (2.3)]. This dosing regimen is based on population modeling and simulation analyses. The exposure associated with this dosing regimen is expected to provide sufficient pharmacodynamic activity to treat humans exposed to myelosuppressive doses of radiation [see Clinical Pharmacology (12.3)]. The safety of Neulasta at a dose of 6 mg has been assessed on the basis of clinical experience in patients with cancer receiving myelosuppressive chemotherapy.

The efficacy of Neulasta for the acute radiation syndrome setting was studied in a randomized, placebo-controlled non-human primate model of radiation injury. Rhesus macaques were randomized to either a control (n = 23) or treated (n = 23) cohort. On study day 0, animals (n = 6 to 8 per irradiation day) were exposed to total body irradiation (TBI) of 7.50 ± 0.15 Gy delivered at 0.8 ± 0.03 Gy/min, representing a dose that would be lethal in 50% of animals by 60 days of follow-up (LD50/60). Animals were administered subcutaneous injections of a blinded treatment (control article [5% dextrose in water] or pegfilgrastim [300-319 mcg/kg/day]) on study day 1 and on study day 8. The primary endpoint was survival. Animals received medical management consisting of intravenous fluids, antibiotics, blood transfusions, and other support as required.

Pegfilgrastim significantly (at 0.0014 level of significance) increased 60-day survival in irradiated non-human primates: 91% survival (21/23) in the pegfilgrastim group compared to 48% survival (11/23) in the control group.

16 HOW SUPPLIED/STORAGE AND HANDLING

Neulasta single-dose prefilled syringe for manual use

Neulasta injection is a clear, colorless solution supplied in a prefilled single-dose syringe for manual use containing 6 mg pegfilgrastim, supplied with a 27-gauge, 1/2-inch needle with an UltraSafe® Needle Guard.

The needle cap of the prefilled syringe contains dry natural rubber (a derivative of latex).

Neulasta is provided in a dispensing pack containing one sterile 6 mg/0.6 mL prefilled syringe (NDC 55513-190-01).

Neulasta prefilled syringe does not bear graduation marks and is intended only to deliver the entire contents of the syringe (6 mg/0.6 mL) for direct administration. Use of the prefilled syringe is not recommended for direct administration for pediatric patients weighing less than 45 kg who require doses that are less than the full contents of the syringe.

STORAGE AND HANDLING

Store refrigerated between 36°F to 46°F (2°C to 8°C) in the carton to protect from light. Do not shake. Discard syringes stored at room temperature for more than 48 hours. Avoid freezing; if frozen, thaw in the refrigerator before administration. Discard syringe if frozen more than once.

Neulasta Onpro® kit

Neulasta Onpro kit is provided in a carton containing one sterile prefilled syringe and one sterile on-body injector (OBI) for Neulasta (NDC 55513-192-01).

The Neulasta injection single-dose prefilled syringe contains 0.64 mL of a clear, colorless solution that delivers 6 mg/0.6 mL of pegfilgrastim when used with the OBI for Neulasta. The prefilled syringe is supplied with a 27-gauge, 1/2-inch needle. The syringe does not bear graduation marks and is only to be used with the OBI for Neulasta.

The needle cap of the prefilled syringe contains dry natural rubber (a derivative of latex).

STORAGE AND HANDLING

Store Neulasta Onpro kit in the refrigerator at 36°F to 46°F (2°C to 8°C) until 30 minutes prior to use. Because the OBI for Neulasta is at room temperature during the period of use, Neulasta Onpro kit should not be held at room temperature longer than 12 hours prior to use. Discard Neulasta Onpro kit if stored at room temperature for more than 12 hours.

Do not use the OBI for Neulasta if its packaging has been previously opened.

17 PATIENT COUNSELING INFORMATION

Advise the patient to read the FDA-approved patient labeling (Patient Information and Instructions for Use).

Advise patients of the following risks and potential risks with Neulasta:

- Splenic rupture and splenomegaly
- Acute Respiratory Distress Syndrome
- Serious allergic reactions
- Sickle cell crisis
- Glomerulonephritis
- Increased risk of Myelodysplastic Syndrome and/or Acute Myeloid Leukemia in patients with breast and lung cancer who receive Neulasta in conjunction with chemotherapy and/or radiation therapy
- Capillary Leak Syndrome
- Aortitis

Advise patients acutely exposed to myelosuppressive doses of radiation (Hematopoietic Subsyndrome of Acute Radiation Syndrome) that efficacy studies of Neulasta for this indication could not be conducted in humans for ethical and feasibility reasons and that, therefore, approval of this use was based on efficacy studies conducted in animals [see Clinical Studies (14.2)].

Instruct patients who self-administer Neulasta using the single-dose prefilled syringe of the:

- Importance of following the Instructions for Use.
- Dangers of reusing syringes.
- Importance of following local requirements for proper disposal of used syringes.

Advise patients on the use of the on-body injector (OBI) for Neulasta:

- Review the Patient Information and Patient Instructions for Use with the patient and provide the instructions to the patient.
- Refer the patient to the dose delivery information written on the Patient Instructions for Use.
- Tell the patient when their dose delivery of Neulasta will begin and when their dose delivery should be completed.
- Advise the patient that serious allergic reactions can happen with Neulasta. Patients should have a caregiver nearby for the first use. Patients should plan to be in a place where they can appropriately monitor the OBI for Neulasta during the approximately 45 minute Neulasta delivery and for an hour after the delivery. Advise the patient to avoid traveling, driving, or operating heavy machinery during hours 26-29 following application of the OBI for Neulasta.
- If the OBI for Neulasta is placed on the back of the arm, remind the patient that a caregiver must be available to monitor the OBI for Neulasta.
- If a patient calls the healthcare provider regarding any OBI for Neulasta problems, the healthcare provider is advised to call Amgen at 1-800-772-6436.
- Advise the patient:
  - to call their healthcare provider immediately if the status light on the OBI for Neulasta is flashing red (see the Patient Instructions for Use).
  - to inform their healthcare provider if the adhesive on the OBI for Neulasta becomes saturated with fluid, or there is dripping, as this may be evidence of significant product leakage, resulting in inadequate or missed dose (see the Patient Instructions for Use).
  - to keep the OBI for Neulasta dry for approximately the last 3 hours prior to the dose delivery start to better enable potential leak detection.
  - that the OBI for Neulasta should only be exposed to temperatures between 41°F and 104°F (5°C-40°C).
  - to keep the OBI for Neulasta at least 4 inches away from electrical equipment such as cell phones, cordless telephones, microwaves, and other common appliances. Failure to keep the OBI for Neulasta at least this recommended distance may interfere with operation and can lead to a missed or incomplete dose of Neulasta.
  - that if the needle is exposed after OBI for Neulasta removal, place the used OBI for Neulasta in a sharps disposal container to avoid accidental needle stick and call their healthcare provider immediately.
  - to remove the OBI for Neulasta after the green light shines continuously and to place the used OBI for Neulasta in a sharps disposal container (see the Patient Instructions for Use).
- Advise the patient:
  - do not reapply the OBI for Neulasta if the OBI for Neulasta comes off before full dose is delivered and instead call their healthcare provider immediately, as they may need a replacement dose.
  - avoid bumping the OBI for Neulasta or knocking the OBI for Neulasta off the body.
  - do not use other materials to hold the on-body injector in place that could cover audio/visual indicators or compress the on-body injector against the patient's skin, as this could dislodge the cannula and lead to a missed dose or incomplete dose of Neulasta.
  - do not expose the OBI for Neulasta to medical imaging studies (e.g., X-ray scan, MRI, CT scan and ultrasound), radiation treatment, and oxygen rich environments such as hyperbaric chambers to avoid OBI for Neulasta damage and patient injury.
- Advise the patient to avoid:
  - airport X-ray scans and request a manual pat down instead; remind patients who elect to request a manual pat down to exercise care to avoid having the OBI for Neulasta dislodged during the pat down process.
  - sleeping on the OBI for Neulasta or applying pressure on the OBI for Neulasta as this may affect OBI for Neulasta performance.
  - getting body lotions, creams, oils, and cleaning agents near the OBI for Neulasta as these products may loosen the adhesive.
  - use of lotions, creams, or oils on their arms and abdomen prior to their next scheduled OBI for Neulasta dose (to help with device adherence to the skin).
  - using bath tubs, hot tubs, whirlpools, or saunas and avoid exposing the OBI for Neulasta to direct sunlight as these may affect the drug.
  - peeling off or disturbing the OBI for Neulasta adhesive before delivery of full dose is complete.

Neulasta® (pegfilgrastim)
Manufactured by:
Amgen Inc.
One Amgen Center Drive
Thousand Oaks, California 91320-1799
U.S. License No. 1080

Patent: http://pat.amgen.com/onpro/

© 2002-2025 Amgen Inc. All rights reserved.
www.neulasta.com
1-800-77-AMGEN (1-800-772-6436)
v28

Patient Information
Neulasta® (nu-las-tah)
(pegfilgrastim)
injection
Single-Dose Prefilled Syringe

What is Neulasta?
Neulasta is a man-made form of granulocyte colony-stimulating factor (G-CSF). G-CSF is a substance produced by the body. It stimulates the growth of neutrophils, a type of white blood cell important in the body's fight against infection.
Acute Radiation Syndrome: The effectiveness of Neulasta for this use was only studied in animals, because it could not be studied in people.

Do not take Neulasta if you have had a serious allergic reaction to pegfilgrastim or filgrastim.

Before you receive Neulasta, tell your healthcare provider about all of your medical conditions, including if you:

- have a sickle cell disorder.
- have kidney problems.
- are allergic to latex. The needle cap on the prefilled syringe contains dry natural rubber (derived from latex). You should not give Neulasta using the prefilled syringe if you have latex allergies.
- are pregnant or plan to become pregnant. It is not known if Neulasta will harm your unborn baby.
- are breastfeeding or plan to breastfeed. It is not known if Neulasta passes into your breast milk.

Tell your healthcare provider about all of the medicines you take, including prescription and over-the-counter medicines, vitamins, and herbal supplements.

How will I receive Neulasta?

- Neulasta is given as an injection under your skin (subcutaneous injection) by a healthcare provider. If your healthcare provider decides that the subcutaneous injections can be given at home by you or your caregiver, follow the detailed "Instructions for Use" that comes with your Neulasta for information on how to prepare and inject a dose of Neulasta.
- You and your caregiver will be shown how to prepare and inject Neulasta before you use it.
- You should not inject a dose of Neulasta to children weighing less than 45 kg from a Neulasta prefilled syringe. A dose less than 0.6 mL (6 mg) cannot be accurately measured using the Neulasta prefilled syringe.
- If you are receiving Neulasta because you are also receiving chemotherapy, the last dose of Neulasta should be injected at least 14 days before and 24 hours after your dose of chemotherapy.
- If you miss a dose of Neulasta, talk to your healthcare provider about when you should give your next dose.

What are possible side effects of Neulasta?
Neulasta may cause serious side effects, including:

- Spleen rupture. Your spleen may become enlarged and can rupture. A ruptured spleen can cause death. Call your healthcare provider right away if you have pain in the left upper stomach area or your left shoulder.
- A serious lung problem called Acute Respiratory Distress Syndrome (ARDS). Call your healthcare provider or get emergency help right away if you have shortness of breath with or without a fever, trouble breathing, or a fast rate of breathing.
- Serious allergic reactions. Neulasta can cause serious allergic reactions. These reactions can cause a rash over your whole body, shortness of breath, wheezing, dizziness, swelling around your mouth or eyes, fast heart rate, and sweating. If you have any of these symptoms, stop using Neulasta and call your healthcare provider or get emergency medical help right away.
- Sickle cell crises. You may have a serious sickle cell crisis, which could lead to death, if you have a sickle cell disorder and receive Neulasta. Call your healthcare provider right away if you have symptoms of sickle cell crisis such as pain or difficulty breathing.
- Kidney injury (glomerulonephritis). Neulasta can cause kidney injury. Call your healthcare provider right away if you develop any of the following symptoms:
  - swelling of your face or ankles
  - blood in your urine or dark colored urine
  - you urinate less than usual
- Increased white blood cell count (leukocytosis). Your healthcare provider will check your blood during treatment with Neulasta.
- Decreased platelet count (thrombocytopenia). Your healthcare provider will check your blood during treatment with Neulasta. Tell your healthcare provider if you have unusual bleeding or bruising during treatment with Neulasta. This could be a sign of decreased platelet counts, which may reduce the ability of your blood to clot.
- Capillary Leak Syndrome. Neulasta can cause fluid to leak from blood vessels into your body's tissues. This condition is called "Capillary Leak Syndrome" (CLS). CLS can quickly cause you to have symptoms that may become life-threatening. Get emergency medical help right away if you develop any of the following symptoms:
  - swelling or puffiness and are urinating less than usual
  - trouble breathing
  - swelling of your stomach area (abdomen) and feeling of fullness
  - dizziness or feeling faint
  - a general feeling of tiredness
- Myelodysplastic syndrome and acute myeloid leukemia. If you have breast cancer or lung cancer, when Neulasta is used with chemotherapy and radiation therapy, or with radiation therapy alone, you may have an increased risk of developing a precancerous blood condition called myelodysplastic syndrome (MDS) or a blood cancer called acute myeloid leukemia (AML). Symptoms of MDS and AML may include tiredness, fever, and easy bruising or bleeding. Call your healthcare provider if you develop these symptoms during treatment with Neulasta.
- Inflammation of the aorta (aortitis). Inflammation of the aorta (the large blood vessel which transports blood from the heart to the body) has been reported in patients who received Neulasta. Symptoms may include fever, abdominal pain, feeling tired, and back pain. Call your healthcare provider if you experience these symptoms.

The most common side effects of Neulasta are pain in the bones, arms, and legs.
These are not all the possible side effects of Neulasta. Call your healthcare provider for medical advice about side effects. You may report side effects to FDA at 1-800-FDA-1088.

How should I store Neulasta?

- Store Neulasta in the refrigerator between 36°F to 46°F (2°C to 8°C).
- Do not freeze.
- Keep the prefilled syringe in the original carton to protect from light or physical damage.
- Do not shake the prefilled syringe.
- Take Neulasta out of the refrigerator 30 minutes before use and allow it to reach room temperature before preparing an injection.
- Throw away (dispose of) any Neulasta that has been left at room temperature, 68°F to 77°F (20°C to 25°C), for more than 48 hours.

Keep the Neulasta prefilled syringe out of the reach of children.

General information about the safe and effective use of Neulasta.
Medicines are sometimes prescribed for purposes other than those listed in a Patient Information leaflet. Do not use Neulasta for a condition for which it was not prescribed. Do not give Neulasta to other people, even if they have the same symptoms that you have. It may harm them. You can ask your pharmacist or healthcare provider for information about Neulasta that is written for health professionals.

What are the ingredients in Neulasta?
Active ingredient: pegfilgrastim
Inactive ingredients: acetate, polysorbate 20, sodium and sorbitol in water for injection.
Manufactured by:
Amgen Inc., One Amgen Center Drive, Thousand Oaks, California 91320-1799
U.S. License No. 1080
Patent: http://pat.amgen.com/onpro/
©2002- 2025 Amgen Inc. All rights reserved.
For more information go to www.neulasta.com, or call 1-800-77-AMGEN (1-800-772-6436).
1xxxxx v17

This Patient Information has been approved by the U.S. Food and Drug Administration.

Revised: 01/2021

Patient Information
Neulasta® (nu-las-tah)
(pegfilgrastim)
injection
On-body injector for Neulasta

What is the most important information I need to know about receiving Neulasta with the on-body injector for Neulasta?

- See the Instructions for Use for the on-body injector for Neulasta for detailed information about the on-body injector for Neulasta and important information about your dose delivery that has been written by your healthcare provider.
  - Know the time that delivery of your dose of Neulasta is expected to start.
  - Avoid traveling, driving, or operating heavy machinery during hour 26 through hour 29 after the on-body injector for Neulasta is applied. Avoid activities and places that may interfere with monitoring during the 45-minute period that Neulasta is expected to be delivered by the on-body injector for Neulasta, and for 1 hour after delivery.
- A caregiver should be with you the first time that you receive Neulasta with the on-body injector for Neulasta.
- Before your next scheduled Neulasta dose, avoid use of lotions, creams, or oils on your arms and stomach area (abdomen) to help keep the device on your skin.
- If placed on the back of the arm, a caregiver must be available to monitor the status of the on-body injector.
- If you have an allergic reaction during the delivery of Neulasta, remove the on-body injector for Neulasta by grabbing the edge of the adhesive pad and peeling off the on-body injector for Neulasta. Get emergency medical help right away.
- You should only receive a dose of Neulasta on the day your healthcare provider tells you.
- You should not receive your dose of Neulasta any sooner than 24 hours after you finish receiving your chemotherapy. The on-body injector for Neulasta is programmed to deliver your dose about 27 hours after your healthcare provider places the on-body injector for Neulasta on your skin.
- Do not expose the on-body injector for Neulasta to the following because the on-body injector for Neulasta may be damaged and you could be injured:
  - Diagnostic imaging (e.g., CT Scan, MRI, Ultrasound, X-ray)
  - Radiation treatment
  - Oxygen rich environments, such as hyperbaric chambers
- Avoid airport X-ray scans. Request a manual pat down instead. Use care during a manual pat down to help prevent the on-body injector for Neulasta from being accidentally removed.
- Keep the on-body injector for Neulasta at least 4 inches away from electrical equipment such as cell phones, cordless telephones, microwaves and other common appliances. If the on-body injector for Neulasta is too close to electrical equipment, it may not work correctly and can lead to a missed or incomplete dose of Neulasta.
- The on-body injector is for adult patients only.
- If your on-body injector is not working properly, you may miss your dose or you may not receive your full dose of Neulasta. If you miss your dose or do not receive your full dose of Neulasta, you may have an increased risk of developing fever or infection.
- Call your healthcare provider right away, as you may need a replacement dose, if any of the following occur:
  - on-body injector for Neulasta comes off before or during a dose delivery. Do not re-apply it.
  - on-body injector for Neulasta is leaking.
  - adhesive on your on-body injector for Neulasta becomes noticeably wet (saturated) with fluid, or there is dripping. This may mean that Neulasta is leaking out of your on-body injector for Neulasta. If this happens you may only receive some of your dose of Neulasta, or you may not receive a dose at all.
  - on-body injector for Neulasta status light is flashing red.

What is Neulasta?
Neulasta is a prescription medicine used to help reduce the chance of infection due to a low white blood cell count, in people with certain types of cancer (non-myeloid), who receive anti-cancer medicines (chemotherapy) that can cause fever and low blood cell count.

Do not take Neulasta if you have had a serious allergic reaction to pegfilgrastim or filgrastim.

Before you receive Neulasta, tell your healthcare provider about all of your medical conditions, including if you:

- have a sickle cell disorder
- have had severe skin reactions to acrylic adhesives
- are allergic to latex. The needle cap on the prefilled syringe contains dry natural rubber (derived from latex).
- have kidney problems
- are pregnant or plan to become pregnant. It is not known if Neulasta may harm your unborn baby.
- are breastfeeding or plan to breastfeed. It is not known if Neulasta passes into your breast milk.

Tell your healthcare provider about all the medicines you take, including prescription and over-the-counter medicines, vitamins, and herbal supplements.

How will I receive Neulasta?
See the Instructions for Use for detailed information about how you will receive a dose of Neulasta with the on-body injector for Neulasta, and how to remove and dispose of the on-body injector for Neulasta.

- See the section "What is the most important information I need to know about receiving Neulasta with the on-body injector for Neulasta?"
- Neulasta is given as an injection under the skin (subcutaneous). Your healthcare provider will use a prefilled syringe with Neulasta to fill the on-body injector prior to applying it. The prefilled syringe with Neulasta and the on-body injector are provided to your healthcare provider as part of Neulasta Onpro® kit. The on-body injector for Neulasta will be applied to the stomach area (abdomen) or back of your arm by your healthcare provider. If the on-body injector for Neulasta was placed on the back of your arm, a caregiver must be available to monitor the on-body injector for Neulasta.
- Your healthcare provider should place the on-body injector for Neulasta on an area of your skin that does not have swelling, redness, cuts, wounds, or abrasions. Tell your healthcare provider about any skin reactions that happen in the on-body injector for Neulasta application area after it has been applied.
- The on-body injector for Neulasta is programmed to deliver your dose about 27 hours after your healthcare provider places the on-body injector for Neulasta on your skin.
- The dose of Neulasta will be delivered over about 45 minutes. During dose delivery and for 1 hour after delivery, it is best to stay in a place where you or a caregiver can monitor the on-body injector for Neulasta to make sure you receive your full dose of Neulasta and watch for symptoms of an allergic reaction.
- Your healthcare provider will show you how to monitor the on-body injector for Neulasta to make sure delivery has been completed.
- Keep the on-body injector for Neulasta dry for about the last 3 hours before the dose delivery is expected to start. This will help you to better detect possible leaking from the on-body injector for Neulasta.
- Only expose the on-body injector for Neulasta to temperatures between 41°F to 104°F (5°C to 40°C).

While the on-body injector for Neulasta is in place you should avoid:

- traveling, driving or operating heavy machinery during hour 26 through hour 29 after the on-body injector for Neulasta is applied.
- sleeping on the on-body injector for Neulasta or applying pressure on the on-body injector for Neulasta. The on-body injector for Neulasta may not work properly.
- bumping the on-body injector for Neulasta or knocking it off your body.
- using other materials to hold the on-body injector in place. Using other materials could cover audio or visual indicators or press the on-body injector against your skin, and lead to a missed dose or incomplete dose of Neulasta.
- getting body lotion, creams, oils, and skin cleansing products near the on-body injector for Neulasta. These products may loosen the adhesive that holds the on-body injector for Neulasta onto your body.
- using bath tubs, hot tubs, whirlpools, or saunas, and direct sunlight. These may affect Neulasta.
- peeling off or disturbing the on-body injector for Neulasta adhesive before you receive your full dose of Neulasta.

What are the possible side effects of Neulasta?
Neulasta may cause serious side effects, including:

- Spleen rupture. Your spleen may become enlarged and can rupture. A ruptured spleen can cause death. Call your healthcare provider right away if you have pain in your left upper stomach area or left shoulder.
- A serious lung problem called Acute Respiratory Distress Syndrome (ARDS). Call your healthcare provider or get emergency medical help right away if you have shortness of breath with or without a fever, trouble breathing, or a fast rate of breathing.
- Serious allergic reactions. Neulasta can cause serious allergic reactions. These reactions can cause a rash over your whole body, shortness of breath, wheezing, dizziness, swelling around your mouth or eyes, fast heart rate and sweating.
  If you have an allergic reaction during the delivery of Neulasta, remove the on-body injector for Neulasta by grabbing the edge of the adhesive pad and peeling off the on-body injector for Neulasta. Get emergency medical help right away.
- Sickle cell crises. You may have a serious sickle cell crisis, which could lead to death, if you have a sickle cell disorder and receive Neulasta. Call your healthcare provider right away if you develop symptoms of sickle cell crisis such as pain or difficulty breathing.
- Kidney injury (glomerulonephritis). Neulasta can cause kidney injury. Call your healthcare provider right away if you develop any of the following symptoms:
  - swelling of your face or ankles
  - blood in your urine or dark colored urine
  - you urinate less than usual
- Increased white blood cell count (leukocytosis). Your healthcare provider will check your blood during treatment with Neulasta.
- Decreased platelet count (thrombocytopenia). Your healthcare provider will check your blood during treatment with Neulasta. Tell your healthcare provider if you have unusual bleeding or bruising during treatment with Neulasta. This could be a sign of decreased platelet counts, which may reduce the ability of your blood to clot.
- Capillary Leak Syndrome. Neulasta can cause fluid to leak from blood vessels into your body's tissues. This condition is called "Capillary Leak Syndrome" (CLS). CLS can quickly cause you to have symptoms that may become life-threatening. Get emergency medical help right away if you develop any of the following symptoms:
  - swelling or puffiness and are urinating less than usual
  - trouble breathing
  - swelling of your stomach-area (abdomen) and feeling of fullness
  - dizziness or feeling faint
  - a general feeling of tiredness
- Myelodysplastic syndrome and acute myeloid leukemia. If you have breast cancer or lung cancer, when Neulasta is used with chemotherapy and radiation therapy, or with radiation therapy alone, you may have an increased risk of developing a precancerous blood condition called myelodysplastic syndrome (MDS) or a blood cancer called acute myeloid leukemia (AML). Symptoms may include tiredness, fever, and easy bruising or bleeding. Call your healthcare provider if you develop these symptoms during treatment with Neulasta.
- Inflammation of the aorta (aortitis). Inflammation of the aorta (the large blood vessel which transports blood from the heart to the body) has been reported in patients who received Neulasta. Symptoms may include fever, abdominal pain, feeling tired, and back pain. Call your healthcare provider if you experience these symptoms.

The most common side effect of Neulasta is pain in your bones, and in your arms, and legs.
These are not all the possible side effects of Neulasta. For more information, ask your healthcare provider or pharmacist.
Call your healthcare provider for medical advice about side effects. You may report side effects to FDA at 1-800-FDA-1088.

General information about the safe and effective use of Neulasta
Medicines are sometimes prescribed for purposes other than those listed in a Patient Information leaflet. If you would like more information about Neulasta, talk with your healthcare provider or pharmacist. You can ask your pharmacist for information about Neulasta that is written for health professionals.

What are the ingredients in Neulasta?
Active ingredient: pegfilgrastim
Inactive ingredients: acetate, polysorbate 20, sodium and sorbitol in Water for Injection
Manufactured by:
Amgen Inc., One Amgen Center Drive, Thousand Oaks, California 91320-1799
US License No. 1080
Patent: http://pat.amgen.com/onpro/
© 2002 to 2025 Amgen Inc. All rights reserved.
For more information, go to www.neulasta.com or call 1-844-696-3852 (1-844-MYNEULASTA).
v8

This Patient Information has been approved by the U.S. Food and Drug Administration.

Revised: 01/2021

Neulasta® (pegfilgrastim) Onpro® kit Healthcare Provider INSTRUCTIONS FOR USE

Guide to Parts
Neulasta Prefilled Syringe

On-body Injector for Neulasta

Important

READ THE FOLLOWING INSTRUCTIONS BEFORE USING NEULASTA ONPRO KIT

Prescribing Information

- See Prescribing Information for information on Neulasta.
- The on-body injector is for adult patients only.
- The on-body injector is not recommended for patients with Hematopoietic Subsyndrome of Acute Radiation Syndrome.
- Neulasta prefilled syringe gray needle cap contains dry natural rubber, which is derived from latex.
- For patients who have had severe skin reactions to acrylic adhesives, consider the benefit:risk profile before administering pegfilgrastim via the on-body injector for Neulasta.

Application Information

- The on-body injector should be applied to intact, non-irritated skin on the abdomen or back of the arm. The back of the arm may only be used if there is a caregiver available to monitor the status of the on-body injector.
- The on-body injector has a self-adhesive backing to attach it to the skin, do not use additional materials to hold it in place as this could dislodge the cannula and lead to a missed or incomplete dose of Neulasta.

Environmental Information

- Do not expose the on-body injector for Neulasta to the following environments as the on-body injector may be damaged and the patient could be injured:
  - Diagnostic imaging (e.g., CT Scan, MRI, Ultrasound, X-ray)
  - Radiation treatment
  - Oxygen rich environments such as hyperbaric chambers

Cautions

- Do not use Neulasta Onpro kit to deliver any other drug product
- Do not use the on-body injector if its packaging has been previously opened, or the expiration date on the carton or any components has passed.
- Do not use if the name Neulasta does not appear on Neulasta Onpro kit carton.
- Do not modify the on-body injector.
- Do not attempt to reapply the on-body injector.
- Do not use if either the on-body injector or prefilled syringe is dropped. Start again with a new kit

Storage Information

- Store the kit in the refrigerator at 36°F to 46°F (2°C to 8°C) until ready for use. If the kit is stored at room temperature for more than 12 hours, do not use. Start again with a new kit.
- Keep the prefilled syringe in the kit carton until use to protect from light.
- Do not freeze the kit.
- Do not separate the components of Neulasta Onpro kit until ready for use.

For all questions, or if a patient calls you regarding any injector problems, call Amgen at 1-800-772-6436.

Step 1: Prepare

A | Place the syringe tray and the on-body injector tray on a clean, well-lit work surface. Allow the syringe and on-body injector to come naturally to room temperature for 30 minutes prior to activating. Do not warm the kit components using a heat source.
B | Choose the patient's injection site. Ask the patient about their ability to monitor and remove the on-body injector.; - Use the left or right side of the abdomen, except for a two-inch area right around navel. - Use the back of upper arm only if there is a caregiver available to monitor the status of the on-body injector. - Apply the on-body injector to intact, non-irritated skin. - Do not apply the on-body injector on surgical sites or areas with scar tissue, moles, or excessive hair. In case of excessive hair, carefully trim hair to get the on-body injector close to the skin. - Do not apply the on-body injector on areas where belts, waistbands, or tight clothing may rub against, disturb, or dislodge the on-body injector. - Do not apply the on-body injector on areas where the on-body injector will be affected by folds in the skin.
C | Clean an area on the injection site larger than the on-body injector adhesive backing.
 | Thoroughly clean the site with alcohol to enhance on-body adherence to the skin.; - Only use alcohol to clean the skin. Make sure the skin is oil-free prior to applying the on-body injector. - Allow the skin to completely dry before attaching the on-body injector. - Do not touch this area again before attaching the on-body injector.
 | Remove Neulasta prefilled syringe from tray.
D
 | For safety reasons:; - Do not grasp the gray needle cap. - Do not grasp the plunger rod.
E | Inspect Neulasta prefilled syringe. Neulasta liquid should always be clear and colorless.; - Do not use if the liquid contains particulate matter or discoloration is observed prior to administration. - Do not use the prefilled syringe if the expiration date has passed. - Do not use if any part appears cracked or broken. - Do not use if the gray needle cap is missing or not securely attached. - Do not remove the gray needle cap until ready to fill the on-body injector. - Do not shake the prefilled syringe.; In all the above cases, start again with a new kit.

Step 2: Fill

A | Remove air bubbles in prefilled syringe. Injecting air bubbles could interfere with proper operation of the on-body injector.; - Remove the gray needle cap. - Gently tap the syringe with your finger until air bubbles rise to the top. - Slowly push air out of the syringe, taking care to not expel medicine. - A small droplet at the tip of the needle during air purging is normal. - Do not recap the syringe.
B | Center the needle directly over the medicine port and insert all the way into the port, avoiding sides.

Insert needle into medicine port at a 90 degree angle only.

- Do not remove the blue needle cover before filling the on-body injector.
- Do not insert the needle more than once.
- Do not bend the needle. Avoid spilling the medicine.

C | Push the plunger rod to empty entire syringe contents into the on-body injector.
 | - During filling, you will hear beeping. - The status light will flash amber. - You now have 3 full minutes to apply the on-body injector to your patient.; Discard used syringe in sharps container.
D | Check to see if the on-body injector is full and the amber light is flashing. You should see a black line next to FULL on the fill indicator. If this is not the case, do not use. Start again with a new Neulasta Onpro kit.
E | Firmly lift and remove the blue needle cover away from the on-body injector.

Step 3: Apply

A

Peel away both pull tabs to show the adhesive. Never touch hands or gloves to the adhesive.
Make sure skin is dry prior to applying the on-body injector.

- Do not pull off the adhesive pad or fold it.
- Do not touch or contaminate the automatic needle area.
- Do not use if the needle or cannula is extended past the adhesive or is extended before the on-body injector is placed on the patient.
- Do not place adhesive on skin that is damp.

B

Before the cannula inserts, securely apply the on-body injector so it is visible and can be monitored by the patient or caregiver.
You now have time to carefully apply the on-body injector without folding or wrinkling the adhesive.

- Do not touch the adhesive.
- Grasp the on-body injector's plastic case with your fingertips and only by sides, keeping fingers off of the adhesive.
- Do not let the adhesive bend or curl while applying the on-body injector to skin.
- Important: Once on the skin, press firmly on the on-body injector to ensure proper adhesion to the patient's skin.
- Press around the entire adhesive so it lies down without folds or wrinkles.
- Hold the top of the on-body injector and run finger around the adhesive to create a secure attachment.
- If additional adhesion is deemed appropriate, an adhesive extender that fits around the on-body injector can be obtained by calling 1-844-MYNEULASTA (1-844-696-3852).
- Do not use other materials to secure the on-body injector to the patient that could cover audio/visual indicators or compress the on-body injector against the patient's skin.

Back of upper arm (triceps)
Vertical with the light facing down toward the elbow

Abdomen
Horizontal with the light facing up and visible to the patient

Do not worry if the on-body injector is quiet.
When 3 minutes are up, the on-body injector will beep telling you the cannula is about to insert.

Step 4: Finish

A | Wait for the status light to turn green. This means the cannula has been inserted. Do not remove the on-body injector during cannula insertion to avoid needle stick injury to you or to the patient.

Check the quality of adhesion before sending the patient home.

If the adhesive is wrinkled in front of the cannula window or has folds anywhere that prevent the on-body injector from securely adhering, remove the on-body injector. Start again with a new kit and call Amgen at 1-800-772-6436.

B | Provide the Patient IFU Booklet for the patient to take home. Fill in the Dose Delivery information on the booklet, and review the following instructions with your patient:; - The on-body injector will always flash a slow green light to let them know it is working properly. - The patient should keep the on-body injector dry for at least 3 hours after it was placed on their skin. - After approximately 27 hours, the dose delivery will begin. Dose delivery will take about 45 minutes, during this time, the on-body injector will flash a fast green light. - When dose delivery is complete, the on-body injector will sound a long beep, and the status light will turn SOLID GREEN. - Do not remove the on-body injector until the status light is SOLID GREEN. - If the red error light is flashing, or the adhesive is noticeably wet (saturated), or the on-body injector is dislodged, the patient should contact their healthcare provider immediately as they may need a replacement dose.
Attention!
What to do if you hear beeping or when you look at status light and it is flashing red.
If at any time the on-body injector beeps continuously for 5 minutes, and the status light is flashing red, take the on-body injector off of the patient.
- Do not apply or leave the on-body injector on the patient if red error light is on.
In all cases, do not use. Start over with a new Neulasta Onpro kit, and call Amgen at 1-800-772-6436.
What to do if your patient reports the status light is flashing red.
If the patient reports the status light is flashing red, they may not have received the full dose. Schedule a follow-up appointment with your patient.
What to do if your patient reports the adhesive is saturated with fluid or the on-body injector is dripping.
If the patient reports an on-body injector leak, they may not have received the full dose. Schedule a follow-up appointment with your patient.

In all cases report the incident to Amgen at 1-800-772-6436.

Neulasta® (pegfilgrastim)

Manufactured by:
Amgen Inc.
One Amgen Center Drive
Thousand Oaks, California 91320-1799
US License No. 1080

Patent: http://pat.amgen.com/onpro/
© 2002 to 2025 Amgen Inc. All rights reserved.

http://www.neulasta.com/
1-844-MYNEULASTA (1-844-696-3852)
Issued: 03/2021
V13

Before You Begin

The following is an overview of on-body injector preparation steps. Read this section first
To prepare and apply the on-body injector, you will use a pre-filled syringe to fill and activate it.
As part of this process, the on-body injector uses lights and sounds as signals to help guide you through the preparation and application process.
As you fill the on-body injector, the status light flashes amber and the on-body injector beeps 3 times.
When the status light flashes amber and the on-body injector beeps, this means it has been properly filled and activated.

After the on-body injector activates, you will have 3 full minutes to remove the blue needle guard and adhesive backing, and then apply the on-body injector to your patient.

- The on-body injector will beep several times prior to inserting the cannula.
- Make sure you have the on-body injector properly secured to your patient before the cannula inserts.

When the status light flashes green, this means the on-body injector has successfully inserted the cannula.

For all questions, or if a patient calls you regarding any on-body injector problems, call Amgen at 1-800-772-6436.
← Turn over to continue with the Instructions for Use

Symbol

Meaning

Do not reuse this on-body injector. Single-use only

Refer to Instructions for Use

Do not use if packaging is damaged

Temperature limitation

Humidity limitation

Expiration date (use by date)

Reference/model number

Lot number

Type BF medical device (protection from electrical shock)

Sterilized by ethylene oxide

Waterproof up to 8 feet for 1 hour

Prescription use only

MR Unsafe

On-body injector for Neulasta® (pegfilgrastim)

Neulasta® (pegfilgrastim) prefilled syringe

Pressure Limitation

Do not expose the on-body injector for Neulasta to the following environments as the on-body injector may be damaged and the patient could be injured:

- Diagnostic imaging (e.g., CT Scan, MRI, Ultrasound, X-ray)
- Radiation treatment
- Oxygen rich environments such as hyperbaric chambers

Electromagnetic Compatibility

The information contained in this section (such as separation distances) is, in general, specifically written in regard to the on-body injector for Neulasta. The numbers provided will not guarantee faultless operation but should provide reasonable assurance of such. This information may not be applicable to other medical electrical equipment; older equipment may be particularly susceptible to interference.

General Notes:

Medical electrical equipment requires special precautions regarding electromagnetic compatibility (EMC), and needs to be installed and put into service according to the EMC information provided in this document.

Portable and mobile RF communications equipment can affect medical electrical equipment.

Cables and accessories not specified within the instructions for use are not authorized. Using cables and/or accessories may adversely impact safety, performance, and electromagnetic compatibility (increased emission and decreased immunity).

Care should be taken if the on-body injector for Neulasta is used adjacent to other electrical equipment; if adjacent use is inevitable, the on-body injector for Neulasta should be observed to verify normal operation in this setting.

Electromagnetic Emissions
The on-body injector for Neulasta is intended for use in the electromagnetic environment specified below. The user of the on-body injector for Neulasta should ensure that it is used in such an environment.
Emissions | Compliance according to | Electromagnetic environment
RF Emissions (CISPR 11) | Group 1 | The on-body injector for Neulasta uses RF energy only for its internal function. Therefore, its RF emissions are very low and are not likely to cause any interference in nearby equipment.
CISPR B Emissions Classification | Class B

Electromagnetic Immunity
The on-body injector for Neulasta is intended for use in the electromagnetic environment specified below. The user of this equipment should ensure that it is used in such an environment.
Immunity Test | IEC 60601 Test Level | Compliance Level | Electromagnetic Environment-Guidance
ESD IEC 61000-4-2 | ±8 kV Contact ±15 kV Air | ±8 kV Contact ±15 kV Air | Floors should be wood, concrete or ceramic tile. If floors are synthetic, the r/h should be at least 30%.
Power Frequency 50/60 Hz Magnetic Field IEC 61000-4-8 | 30 A/m | 30 A/m | Power frequency magnetic fields should be that of typical commercial or hospital environment.
Radiated RF Fields 61000-4-3 | 3 V/m 80 MHz to 2.7 GHz | (E1)=3 V/m | Portable and mobile communications equipment should be separated from the on-body injector for Neulasta by no less than the distances calculated/listed below: D=(3.5/V1)(√P)150 kHz to 80 MHz D=(3.5/E1)(√P)80 to 800 MHz D=(7/E1)(√P)800 MHz to 2.5 GHz Where P is the max power in watts and D is the recommended separation distance in meters. Field strengths from fixed transmitters, as determined by an electromagnetic site survey, should be less than the compliance levels (V1 and E1). Interference may occur in the vicinity of equipment containing a transmitter.

Test specifications for ENCLOSURE PORT IMMUNITY to RF wireless communications equipment
The on-body injector for Neulasta is intended for use in the radio frequency environment specified below. The user of this equipment should ensure that it is used in such an environment.
Test Frequency | Band [For some services, only the uplink frequencies are included.] | Service | Modulation [The carrier shall be modulated using a 50% duty cycle square wave signal.] | Maximum Power | Distance | Immunity Test Level
(MHz) | (MHz) |  |  | (W) | (m) | (V/m)
385 | 380-390 | TETRA 400 | Pulse modulation 18 Hz | 1.8 | 0.3 | 27
450 | 430-470 | GMRS 460, FRS 460 | FM [As an alternative to FM modulation, 50% pulse modulation at 18 Hz may be used because while it does not represent actual modulation, it would be worst case.] ± 5 kHz deviation 1 kHz sine | 2 | 0.3 | 28
710 | 704-787 | LTE Band 13, 17 | Pulse modulation 217 Hz | 0.2 | 0.3 | 9
745 | 704-787 | LTE Band 13, 17 | Pulse modulation 217 Hz | 0.2 | 0.3 | 9
780 | 704-787 | LTE Band 13, 17 | Pulse modulation 217 Hz | 0.2 | 0.3 | 9
810 | 800-960 | GSM 800/900, TETRA 800, iDEN 820, CDMA 850, LTE Band 5 | Pulse modulation 18 Hz | 2 | 0.3 | 28
870 | 800-960 | GSM 800/900, TETRA 800, iDEN 820, CDMA 850, LTE Band 5 | Pulse modulation 18 Hz | 2 | 0.3 | 28
930 | 800-960 | GSM 800/900, TETRA 800, iDEN 820, CDMA 850, LTE Band 5 | Pulse modulation 18 Hz | 2 | 0.3 | 28
1720 | 1700-1990 | GSM 1800; CDMA 1900; GSM 1900; DECT; LTE Band 1, 3, 4, 25; UMTS | Pulse modulation 217 Hz | 2 | 0.3 | 28
1845 | 1700-1990 | GSM 1800; CDMA 1900; GSM 1900; DECT; LTE Band 1, 3, 4, 25; UMTS | Pulse modulation 217 Hz | 2 | 0.3 | 28
1970 | 1700-1990 | GSM 1800; CDMA 1900; GSM 1900; DECT; LTE Band 1, 3, 4, 25; UMTS | Pulse modulation 217 Hz | 2 | 0.3 | 28
2450 | 2400-2570 | Bluetooth, WLAN, 802.11 b/g/n, RFID 2450, LTE Band 7 | Pulse modulation 217 Hz | 2 | 0.3 | 28
5240 | 5100-5800 | WLAN 802.11 a/n | Pulse modulation 217 Hz | 0.2 | 0.3 | 9
5500 | 5100-5800 | WLAN 802.11 a/n | Pulse modulation 217 Hz | 0.2 | 0.3 | 9
5785 | 5100-5800 | WLAN 802.11 a/n | Pulse modulation 217 Hz | 0.2 | 0.3 | 9
NOTE If necessary to achieve the IMMUNITY TEST LEVEL, the distance between the transmitting antenna and the ME EQUIPMENT OF ME SYSTEM may be reduced to 1 m. The 1 m test distance is permitted by IEC 61000-4-3.

Recommended separation distances between portable and mobile RF communications equipment and the on-body injector for Neulasta
You can help prevent electromagnetic interference by maintaining a minimum distance between portable and mobile RF communications equipment (transmitters) and the on-body injector for Neulasta, as recommended below, according to the maximum power of the communication equipment.
Rated maximum output power of transmitter, in watts | Separation distance according to frequency of transmitter, in meters
Rated maximum output power of transmitter, in watts | 150 kHz to 80 MHz | 80 MHz to 800 MHz | 800 MHz to 2.5 GHz
Rated maximum output power of transmitter, in watts | D=(3.5/V1)(√P) | D=(3.5/E1)(√P) | D=(7/E1)(√P)
0.01 | 0.11667 | 0.11667 | 0.23333
0.1 | 0.36894 | 0.36894 | 0.73785
1 | 1.1667 | 1.1667 | 2.3333
10 | 3.6894 | 3.6894 | 7.3785
100 | 11.667 | 11.667 | 23.333

Instructions for Use
Neulasta (nu-las-tah)
(pegfilgrastim)
Injection, for subcutaneous use
Single-Dose Prefilled Syringe

Guide to parts

Important: The needle is covered by the gray needle cap before use.

Important

Read the Patient Information for important information you need to know about Neulasta before using these Instructions for Use.

Before you use a Neulasta prefilled syringe, read this important information.

Storing the prefilled syringe

- Store Neulasta in the refrigerator between 36°F to 46°F (2°C to 8°C).
- Do not freeze.
- Keep the prefilled syringe in the original carton to protect from light or physical damage.
- Take the prefilled syringe out of the refrigerator 30 minutes before use and allow it to reach room temperature before preparing an injection.
- Throw away (dispose of) any Neulasta that has been left at room temperature, 68°F to 77°F (20°C to 25°C), for more than 48 hours.
- Keep the Neulasta prefilled syringe out of the reach of children.

Using the prefilled syringe

- It is important that you do not try to give the injection unless you or your caregiver has received training from your healthcare provider.
- Make sure the name Neulasta appears on the carton and prefilled syringe label.
- Check the carton and prefilled syringe label to make sure the dose strength is 6 mg.
- You should not inject a dose of Neulasta to children weighing less than 45 kg from a Neulasta prefilled syringe. A dose less than 0.6 mL (6 mg) cannot be accurately measured using the Neulasta prefilled syringe.
- Do not use a prefilled syringe after the expiration date on the label.
- Do not shake the prefilled syringe.
- Do not remove the gray needle cap from the prefilled syringe until you are ready to inject.
- Do not use the prefilled syringe if the carton is open or damaged.
- Do not use a prefilled syringe if it has been dropped on a hard surface. The prefilled syringe may be broken even if you cannot see the break. Use a new prefilled syringe.
- Do not slide the blue safety guard over the needle before you give the injection. This will "activate" or lock the blue safety guard. Use another prefilled syringe that has not been activated and is ready to use.
- The gray needle cap on the prefilled syringe contains dry natural rubber (made from latex). Tell your healthcare provider if you are allergic to latex. You should not give Neulasta using the prefilled syringe if you have latex allergies.

Call your healthcare provider if you have any questions.

Step 1: Prepare

A Remove the prefilled syringe carton from the refrigerator.

Put the original carton with any unused prefilled syringes back in the refrigerator.

Remove the syringe tray from the carton. On a clean, well-lit surface, place the syringe tray at room temperature for 30 minutes before you give an injection.

- Do not use the prefilled syringe if the carton is damaged.
- Do not try to warm the prefilled syringe by using a heat source such as hot water or microwave.
- Do not leave the prefilled syringe in direct sunlight.
- Do not shake the prefilled syringe.

Open the tray by peeling away the cover. Grab the blue safety guard to remove the prefilled syringe from the tray.

For safety reasons:

- Do not grab the plunger rod.
- Do not grab the gray needle cap.

B Inspect the medicine and prefilled syringe.

Make sure the medicine in the prefilled syringe is clear and colorless.

- Do not use the prefilled syringe if:
  - The medicine is cloudy or discolored or contains flakes or particles.
  - Any part appears cracked or broken.
  - The prefilled syringe has been dropped.
  - The gray needle cap is missing or not securely attached.
  - The expiration date printed on the label has passed.

In all cases, use a new prefilled syringe and call your healthcare provider.

C Gather all materials needed for the injection.

Wash your hands thoroughly with soap and water.

On a clean, well-lit work surface, place the:

- Prefilled syringe
- Alcohol wipe
- Cotton ball or gauze pad
- Adhesive bandage
- Sharps disposal container

Step 2: Get ready

D Prepare and clean the injection site(s).

You can use:

- Thigh
- Stomach area (abdomen), except for a 2-inch area right around the navel (belly button)
- Upper outer area of the buttocks (only if someone else is giving you the injection)
- Outer area of upper arm (only if someone else is giving you the injection)

Clean the injection site with an alcohol wipe. Let the skin dry.

- Do not touch this area again before injecting.
- If you want to use the same injection site, make sure it is not the same spot on the injection site you used for a previous injection.
- Do not inject into areas where the skin is tender, bruised, red, or hard. Avoid injecting into areas with scars or stretch marks.

E Hold the prefilled syringe by the syringe barrel. Carefully pull the gray needle cap straight off and away from the body.

- Do not remove the gray needle cap from the prefilled syringe until you are ready to inject.
- Do not twist or bend the gray needle cap.
- Do not hold the prefilled syringe by the plunger rod.
- Do not put the gray needle cap back onto the prefilled syringe.

Important: Throw the gray needle cap into the sharps disposal container.

Step 3: Subcutaneous (under the skin) injection

F Pinch the injection site to create a firm surface.

Important: Keep skin pinched while injecting.

G Hold the pinch. Insert the needle into the skin at 45 to 90 degrees.

H Using slow and constant pressure, push the plunger rod until it reaches the bottom.

When done, gently pull the syringe off of the skin.

Important: When you remove the syringe, if it looks like the medicine is still in the syringe barrel, this means you have not received a full dose. Call your healthcare provider right away.

Step 4: Finish

I

For your safety, pull the blue safety guard until it clicks and covers the needle.

Once extended, the blue safety guard will lock into position and will not slide back over the needle.

Keep your hands away from the needle at all times.

J Discard (throw away) the used prefilled syringe.

- Put the used prefilled syringe in a FDA-cleared sharps disposal container right away after use. Do not throw away (dispose of) the syringe in the household trash.
- If you do not have a FDA-cleared sharps disposal container, you may use a household container that is:
  - made of a heavy-duty plastic,
  - can be closed with a tight-fitting, puncture-resistant lid, without sharps being able to come out,
  - upright and stable during use,
  - leak-resistant, and
  - properly labeled to warn of hazardous waste inside the container.
- When your sharps disposal container is almost full, you will need to follow your community guidelines for the right way to dispose of your sharps disposal container. There may be state or local laws about how you should throw away used needles and syringes. For more information about safe sharps disposal, and for specific information about sharps disposal in the state that you live in, go to the FDA's website at: http://www.fda.gov/safesharpsdisposal
- Do not reuse the prefilled syringe.
- Do not recycle the prefilled syringe or sharps disposal container or throw them into household trash.

Important: Always keep the sharps disposal container out of the reach of children.

K Examine the injection site.

If there is blood, press a cotton ball or gauze pad on the injection site. Do not rub the injection site. Apply an adhesive bandage if needed.

This Instructions for Use has been approved by the U.S. Food and Drug Administration.

Manufactured by:

Amgen Inc.
One Amgen Center Drive
Thousand Oaks, California 91320-1799
U.S. License No. 1080

Patent: http://pat.amgen.com/onpro/

© 2002-2025 Amgen Inc. All rights reserved.
1xxxxxx
Revised: 01/2025 v3

Patient INSTRUCTIONS FOR USE Neulasta® Onpro® (nu-las-tah) (pegfilgrastim) injection Single-Use On-body Injector

Your On-body injector was applied:

AM

Day

Time

PM

Injection of your dose (delivery) will start around:

AM

Day

Time

PM

Healthcare Provider name:

Healthcare Provider contact number:

On-body Injector lot number:

AMGEN

Neulasta®
(pegfilgrastim)
Onpro®
kit

Get to Know Your On-body Injector

Parts and Signals

Status Light

Flashing Green:
The on-body injector is working properly.
Do not remove the on-body injector if the status light is flashing green.

Solid Green (or off):
Signals dose delivery is complete.
Check to see if fill indicator reads empty.

Flashing Red:
On-body injector error.
If you hear beeping at any time, check the status light. If it is flashing red, call your healthcare provider right away as you may need a replacement dose.

Fill Indicator:
Black line shows how much Neulasta is in the on-body injector.

Contents

IMPORTANT INFORMATION
Learn about your Neulasta On-body Injector.

INFO

STEP 1: MONITOR
What to expect from your device for most of the day.

STEP 2: OBSERVE
What to watch for during dose delivery and what to do if there is an issue.

STEP 3: VERIFY
Understand when delivery is complete and when you may remove the device.

STEP 4: FINISH
Confirm the dose was delivered and dispose of the device.

FAQ
When it is safe to remove your on-body injector and answers to frequently asked questions.

Important Information

On-body Injector for Neulasta Description

INFO

- The on-body injector for Neulasta is intended for delivery of Neulasta. This on-body injector delivers Neulasta with an injection under-the-skin (subcutaneous). See the Patient Information that comes with your on-body injector for important information.
- Your healthcare provider will use a prefilled syringe with Neulasta to fill the on-body injector prior to applying it. The prefilled syringe with Neulasta and the on-body injector are provided to your healthcare provider as part of Neulasta Onpro kit. The on-body injector is applied directly to your skin using a self-adhesive backing. The on-body injector lets you know its status with sounds and lights.

Warnings

- You should only receive a dose of Neulasta on the day your healthcare provider tells you.
- You should not receive your dose of Neulasta any sooner than 24 hours after you finish receiving your chemotherapy. The on-body injector for Neulasta is programmed to deliver your dose about 27 hours after your healthcare provider places the on-body injector on your skin.
- If you have concerns about your medicine, call your healthcare provider right away. Serious allergic reactions can happen with Neulasta. Ask your caregiver to be nearby for the first use. Plan to be in a place where you or your caregiver can closely monitor the on-body injector for Neulasta for about 45-minutes during Neulasta delivery and for an hour after the delivery.
- Do not take Neulasta if you have had a serious allergic reaction to pegfilgrastim (Neulasta) or to filgrastim (Neupogen).

- Tell your healthcare provider if you are allergic to latex. A prefilled syringe is used to fill the on-body injector by your healthcare provider prior to applying the on-body injector. The prefilled syringe gray needle cap contains dry natural rubber, which is derived from latex. Latex may be transferred to your skin.
- Tell your healthcare provider if you have had severe skin reactions to acrylic adhesives.
- If you have an allergic reaction during the delivery of Neulasta, remove the on-body injector by grabbing the edge of the adhesive pad and peeling off the on-body injector. Get emergency medical help right away.
- Call your healthcare provider right away if you have severe pain or skin discomfort around your on-body injector.
- Call your healthcare provider right away if you have pain in your left upper stomach area or left shoulder area. This pain could mean your spleen is enlarged or ruptured.
- Call your healthcare provider or get emergency medical help right away if you get any of these symptoms of acute respiratory distress syndrome (ARDS): fever, shortness of breath, trouble breathing, or a fast rate of breathing.
- Call your healthcare provider right away if you experience any of these symptoms of kidney injury (glomerulonephritis): puffiness in your face or ankles, blood in your urine or brown colored urine or you notice you urinate less than usual.
- Call your healthcare provider if you have persistent or worsening redness or tenderness at the application site (may be a sign of infection).
- The on-body injector is for adult patients only.

Important Information
Wearing the On-body Injector

- This on-body injector delivers Neulasta with an under-the-skin (subcutaneous) injection.
- The on-body injector is small, for one-time use, lightweight, battery-powered, and waterproof up to 8 feet for 1 hour.
- The on-body injector can be worn in a shower. After showering, check the on-body injector to ensure it has not become loose (dislodged).
- Avoid getting body lotions, creams, oils or cleaning agents near the on-body injector as these products may loosen the adhesive. Before your next scheduled Neulasta dose, avoid use of lotions, creams, or oils on your arms and stomach area (abdomen).
- Only expose the on-body injector to temperatures between 41°F and 104°F (5°C and 40°C).
- Do not use bath tubs, hot tubs, whirlpools, or saunas while wearing the on-body injector. This may affect your medicine.
- Do not expose the on-body injector to direct sunlight. If the on-body injector is exposed to direct sunlight for more than 1 hour, it may affect your medicine. Wear the on-body injector under clothing.
- Do not sleep on the on-body injector or apply pressure during wear, especially during dose delivery. This may affect on-body injector performance.
- Do not peel off or disturb the on-body injector adhesive before your full dose is complete. This may result in a missed or incomplete dose of Neulasta.

Environmental Precautions

- Do not expose the on-body injector to the following because the on-body injector may be damaged and you could be injured:
  - Diagnostic imaging (e.g., CT Scan, MRI, Ultrasound, X-ray)
  - Radiation treatment
  - Oxygen rich environments, such as hyperbaric chambers

1

- Keep the on-body injector at least 4 inches away from electrical equipment such as cell phones, cordless telephones, microwaves and other common appliances. Failure to keep the on-body injector at least this recommended distance may interfere with operation and can lead to a missed or incomplete dose of Neulasta.
- Avoid activities and places that may interfere with monitoring during the dosing of Neulasta administered by the on-body injector. For example, avoid traveling, driving, or operating heavy machinery during hours 26-29 following application of the on-body injector for Neulasta (this includes the 45-minute dose delivery period plus an hour post-delivery).
- If you must travel by airplane before the approximately 45-minute dose delivery period with the on-body injector, avoid airport X-ray scans. Request a manual pat down instead. Use care during a manual pat down to help prevent the on-body injector from being accidentally removed. For more information go to: http://www.tsa.gov/traveler-information/travelers-disabilities-and-medical-conditions

A healthcare provider who is familiar with Neulasta should answer your questions. For general questions or support call 1-844-MYNEULASTA (1-844-696-3852) or visit www.neulasta.com.

Step 1: Monitor On-body Injector

 | A | For the next 27 hours, occasionally check the status light for at least 10 seconds. If the status light is flashing green, it is okay.
1
 |  | - Keep the on-body injector and adhesive backing dry for at least 3 hours after it was placed on your skin, and for 3 hours prior to dose delivery. - Be careful not to bump the on-body injector, or knock the on-body injector off your body. - The on-body injector has a self-adhesive backing to attach it to the skin. Do not add other materials to hold it in place as this could dislodge the cannula and lead to a missed or incomplete dose of Neulasta.
 |  | - If the on-body injector was placed on the back of your arm, a caregiver must be available to monitor the status of the on-body injector. - If the on-body injector comes away from your skin at any time, do not reapply it. Call your healthcare provider right away as you may need a replacement dose. - If you hear beeping at any time, check the status light. If it is flashing red, call your healthcare provider right away, as you may need a replacement dose. | 2

Step 2: Observe Dose Delivery

A

After about 27 hours, your on-body injector will begin to deliver your dose of Neulasta.

- Dose delivery will take around 45-minutes to complete. The on-body injector will flash a fast, green light.
- You may hear a series of clicks. This is okay.

2

- When dose delivery is complete, a long beep will sound and the status light will turn solid green.
- If you hear beeping at any time, check the status light. If it is flashing red, call your healthcare provider right away, as you may need a replacement dose.
- Do not remove the on-body injector if the status light is flashing green.

Check your on-body injector often for leaks during the 45-minute dose delivery. If the on-body injector was placed on the back of your arm, a caregiver must be available to check your on-body injector.

- If the adhesive is noticeably wet or dripping with medicine, call your healthcare provider right away, as you may need a replacement dose.

3

Step 3: Verify Dose Complete

 | A | After the beep, check the color of the status light.
3 |  | Check to see if the status light is SOLID GREEN or has switched off. This means the dose is complete. If the dose is complete, go to the next step. Do not remove the on-body injector if the status light is flashing green. | If you see the status light is FLASHING RED, and your on-body injector is beeping, your on-body injector is not functioning properly. Call your healthcare provider right away, as you may need a replacement dose.
B | Grab the edge of the adhesive pad. Slowly peel off the on-body injector.
 |  |  |  | 4
 | - Do not grasp the on-body injector itself to try to pull it off of your body. - If medicine has leaked or the adhesive is noticeably wet or dripping, call your healthcare provider right away, as you may not have received your full dose and you may need a replacement dose. - Remove any extra adhesive using soap and water.

Step 4: Finish

 |  | Check to see if your on-body injector is empty.
4 |  | - Check your status light. Watch for at least 10 seconds. If the status light is solid green or it has switched off, it is okay. - You should see a black line next to the EMPTY indicator. If the on-body injector is not empty, call your healthcare provider right away, as you may need a replacement dose. - If you hear beeping, or when you check the status light and it is flashing red, call your healthcare provider right away. - If the needle is exposed, call your healthcare provider right away.
A | Check off the box below to record how your on-body injector looks after use.
 | ⃞ | Status light is solid green or the status light has switched off. This means that the delivery is complete.
 | ⃞ | On-body injector leaked, call your healthcare provider right away, as you may need a replacement dose.
 | ⃞ | Status light is red, call your healthcare provider right away, as you may need a replacement dose.
B | Properly dispose of the on-body injector.
 | - After on-body injector removal, place the on-body injector in a sharps disposal container whether the needle is exposed or not. - The on-body injector contains batteries, electronics, and a needle. Put the on-body injector in a FDA-cleared sharps disposal container right away after use. Do not throw away (dispose of) the on-body injector in your household trash. - If you do not have a FDA-cleared sharps disposal container, you may use a household container that is: - made of a heavy-duty plastic, - can be closed with a tight-fitting, puncture-resistant lid, without sharps being able to come out, - upright and stable during use, - leak-resistant, and - properly labeled to warn of hazardous waste inside the container - When your sharps disposal container is almost full, you will need to follow your community guidelines for the right way to dispose of your sharps disposal container. There may be state or local laws about how you should throw away used needles and syringes. - Do not dispose of your used sharps disposal container in your household trash unless your community guidelines permit this. Do not recycle your used sharps disposal container. - For more information about safe sharps disposal, and for specific information about sharps disposal in the state that you live in, go to FDA's website at: http://www.fda.gov/safesharpsdisposal.
 | - To participate in Amgen's voluntary disposal program, please call 1-844-MYNEULASTA (1-844-696-3852) or visit www.neulasta.com to enroll. |  |  | FAQ
 | - Keep the used on-body injector and sharps disposal container away from children.

Frequently Asked Questions

How do I know it is safe to remove the on-body injector?

It is safe to remove the on-body injector after checking the following:

- The status light should be solid green.
- If the status light is flashing green, the dose delivery is not complete. Wait until you hear a long beep and the status light turns solid green before removing your on-body injector.
- The status light turns off 1 hour after delivery completion

- The fill indicator should have a black line next to EMPTY

FAQ

What to do if you hear beeping or when you look at the status light and it is flashing red?

- If the status light is flashing red, you may not have received your full dose and may need a replacement dose. Call your healthcare provider right away.

What do I do if the on-body injector comes off before the full dose is delivered?

- Call your healthcare provider right away if the on-body injector at any time comes away from your skin before your full dose delivery, as you may need a replacement dose. Do not reapply it.

What if there is blood at my application site after the on-body injector has been removed?

- If there is blood, press a clean cotton ball or gauze pad on the application site. Apply an adhesive bandage if needed.

What if my application site is red or tender after on-body injector removal?

- Call your healthcare provider right away if you experience persistent or worsening redness or tenderness at the application site, as this can be a sign of infection.

Notes

Neulasta® Onpro®

Patient INSTRUCTIONS FOR USE

Neulasta® (pegfilgrastim)

Manufactured by:
Amgen Inc.
One Amgen Center Drive
Thousand Oaks, California 91320-1799
US License No. 1080

Patent: http://pat.amgen.com/onpro/

© 2002 to 2025 Amgen Inc. All rights reserved.

http://www.neulasta.com

1-844-MYNEULASTA (1-844-696-3852)
Revised: 11/2020
V10

PRINCIPAL DISPLAY PANEL - Kit Carton

1 - Single Dose Neulasta Prefilled Syringe

1 - Sterile On-body Injector for Neulasta

NDC 55513-192-01

AMGEN

Neulasta®
(pegfilgrastim) injection
Onpro®
kit

Pegylated Recombinant Methionyl Human Granulocyte
Colony-Stimulating Factor (PEG-r-metHuG-CSF) derived from E. Coli

6 mg/
0.6 mL*

6 mg/0.6 mL*

* Prefilled syringe contains 0.64 mL to deliver
6 mg/0.6 mL when used with on-body injector

For Subcutaneous Use Only

Carton Contents (intended to be dispensed as a unit):

- 1 sterile On-body Injector for Neulasta
- 1 Neulasta prefilled syringe labeled for use with on-body injector only
- 1 patient instructions for use
- 1 healthcare provider instructions for use, 1 package insert

This Product Contains Dry Natural Rubber
Store at 2° to 8°C (36° to 46°F).
Do Not Freeze or Shake.
Keep in Carton to Protect from Light.

See package insert for full prescribing
information and Instructions for Use

Rx Only

PACKAGE LABEL

Principal Display Panel

NDC 55513-190-01

1 - 0.6 mL Single Dose Prefilled Syringe

AMGEN®

Neulasta ®

(pegfilgrastim) injection

Pegylated Recombinant Methionyl Human Granulocyte Colony-Stimulating Factor

(PEG-r-metHuG-CSF) derived from E Coli

6 mg

6 mg in 0.6 mL Single Dose Prefilled Syringe

For Subcutaneous Use Only

This Product Contains Dry Natural Rubber

Sterile Solution – No Preservative

Rx Only

Manufactured by Amgen Inc.

Thousand Oaks, CA 91320-1799 U.S.A.

U.S. License No. 1080